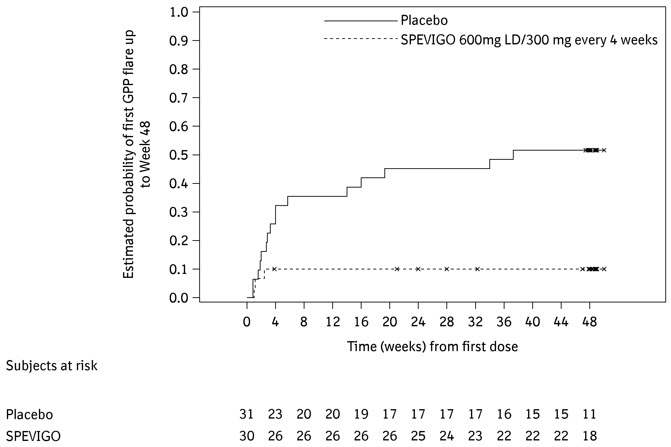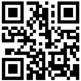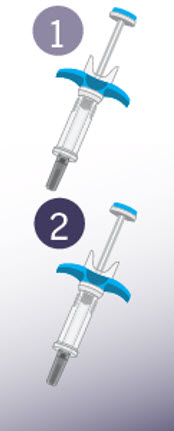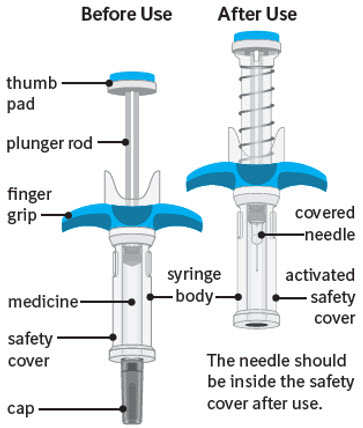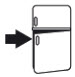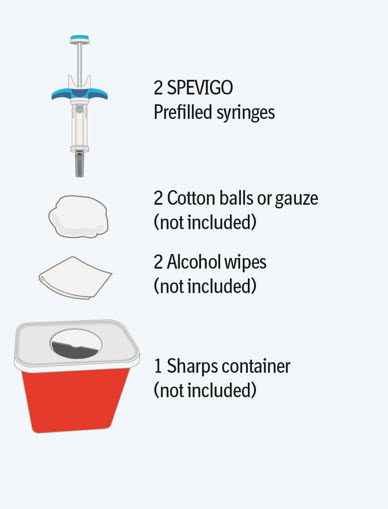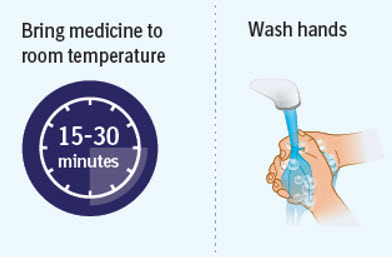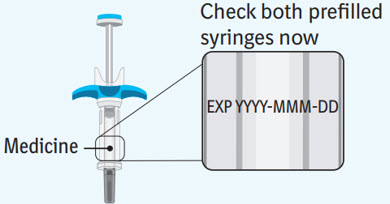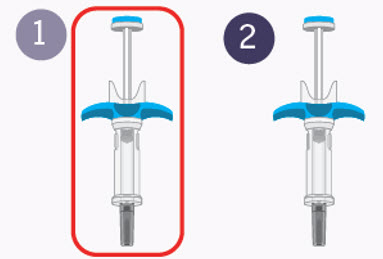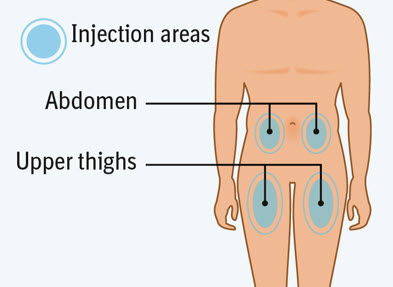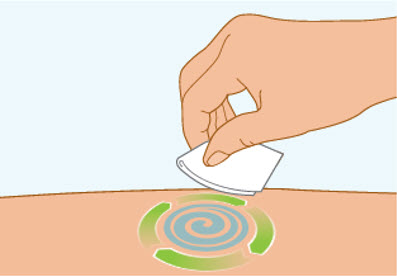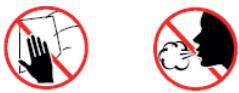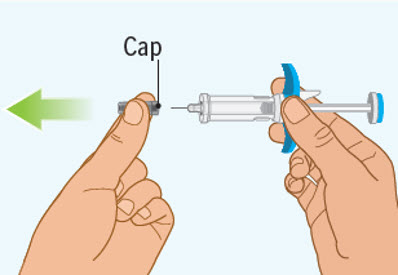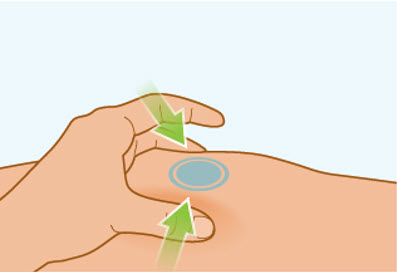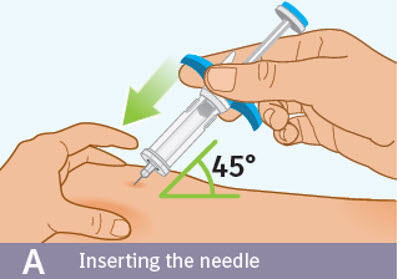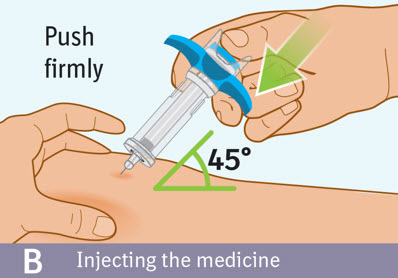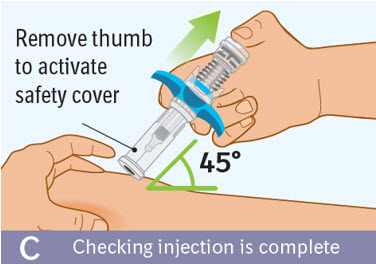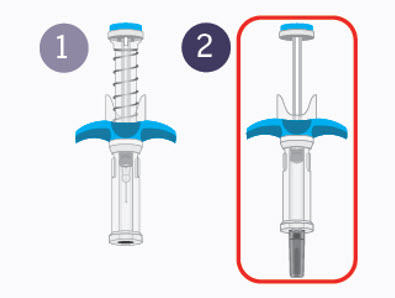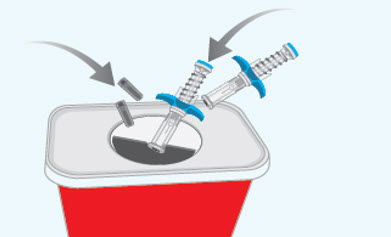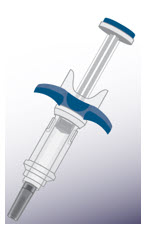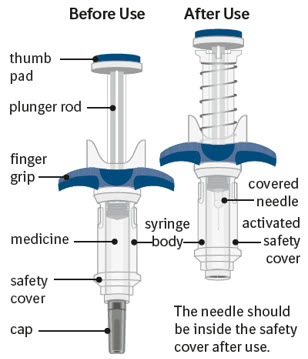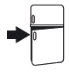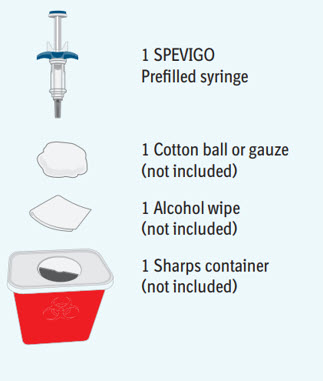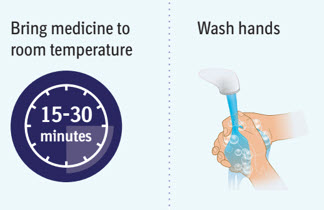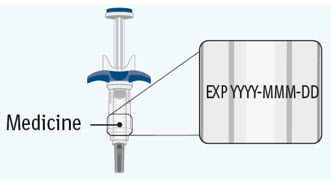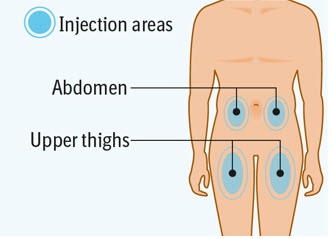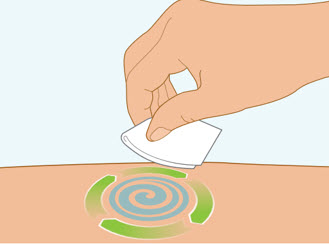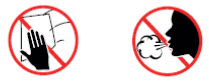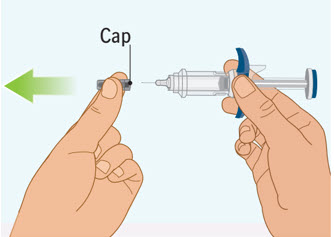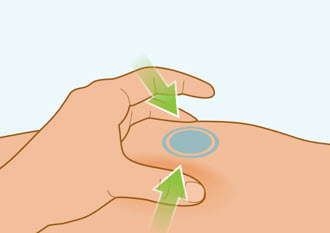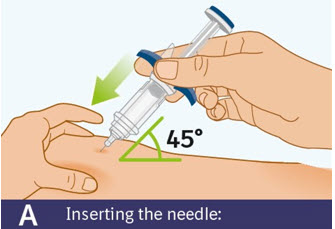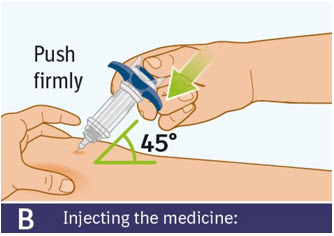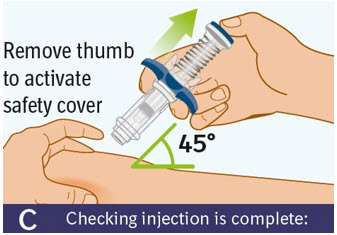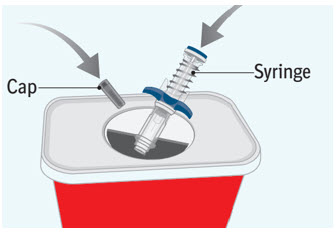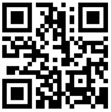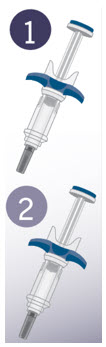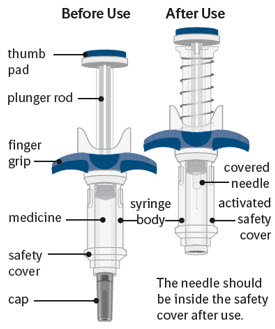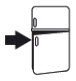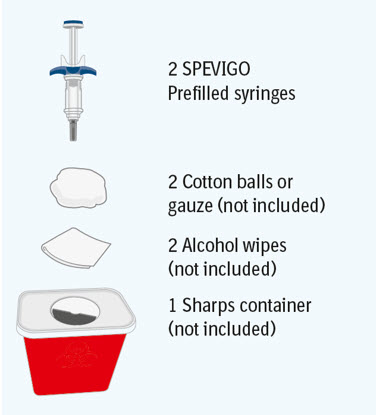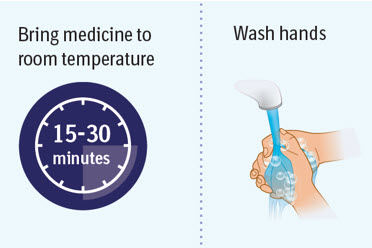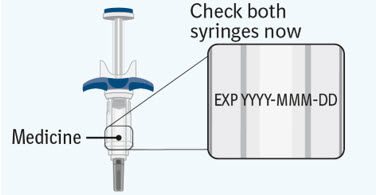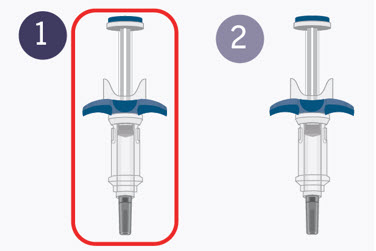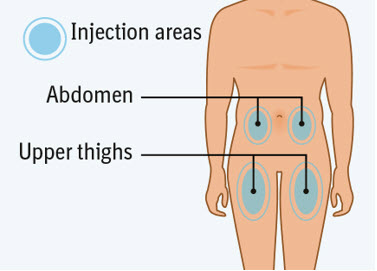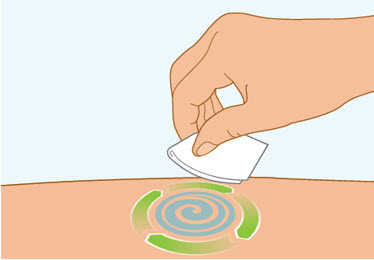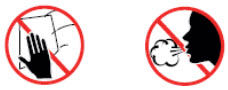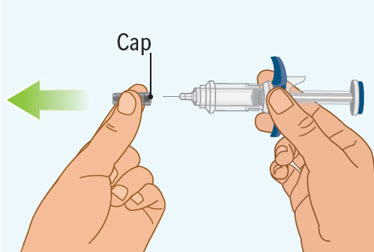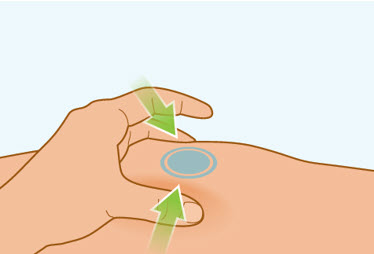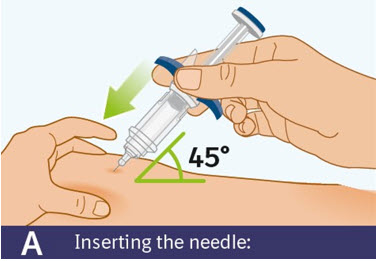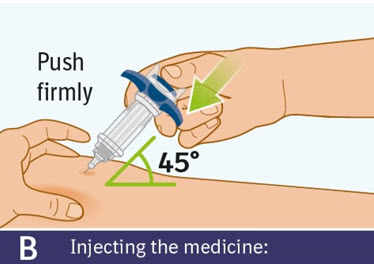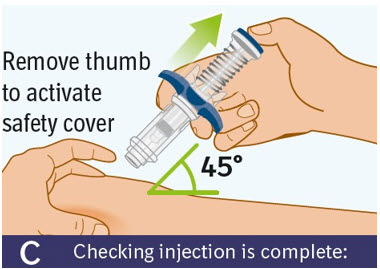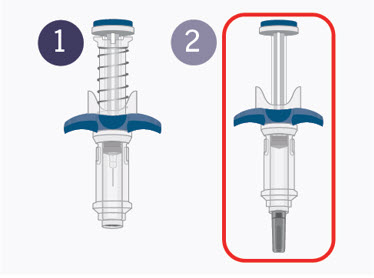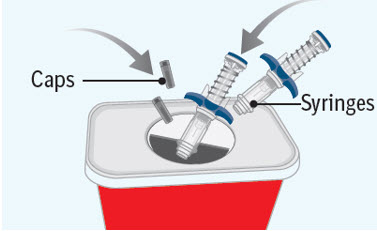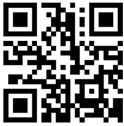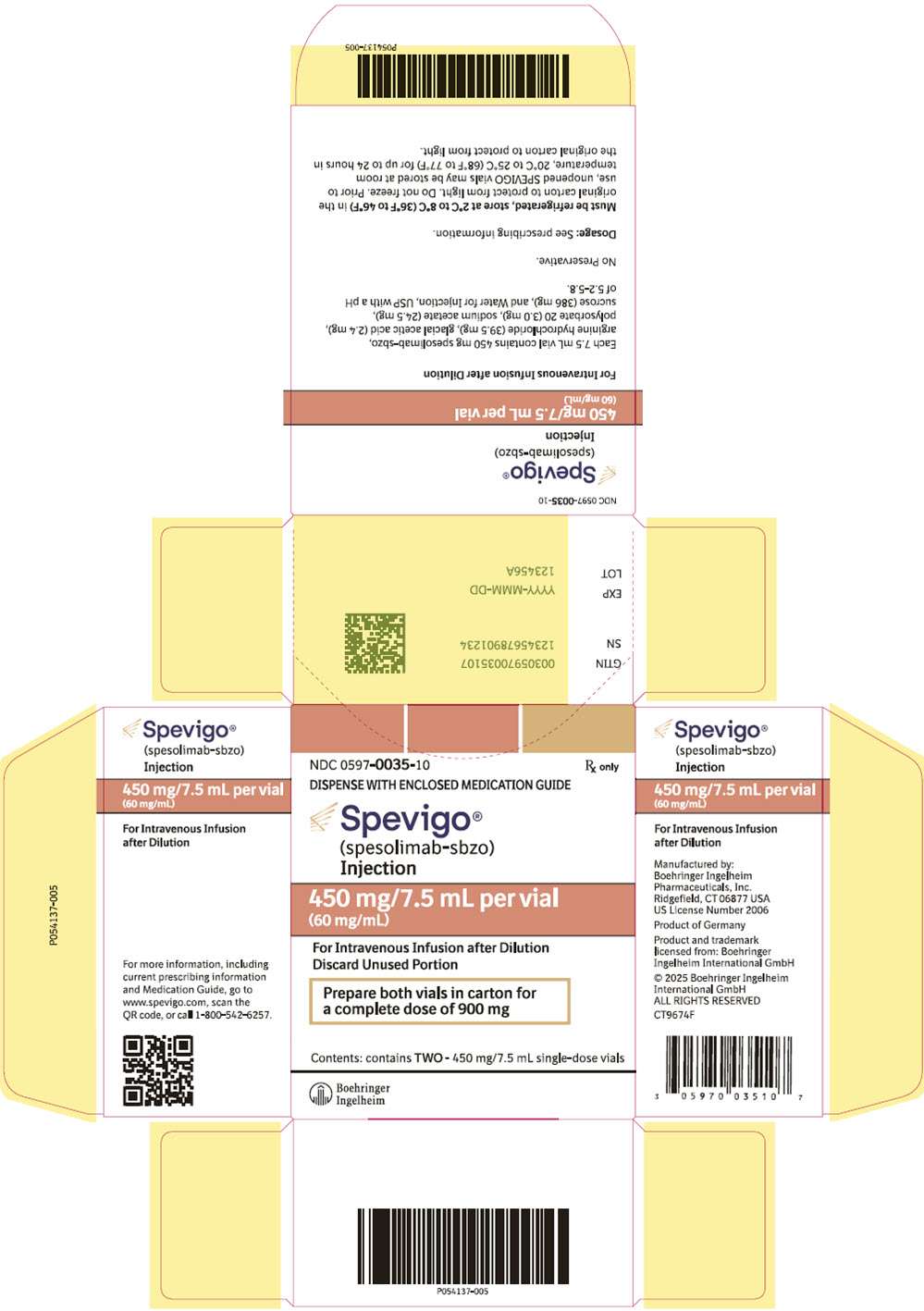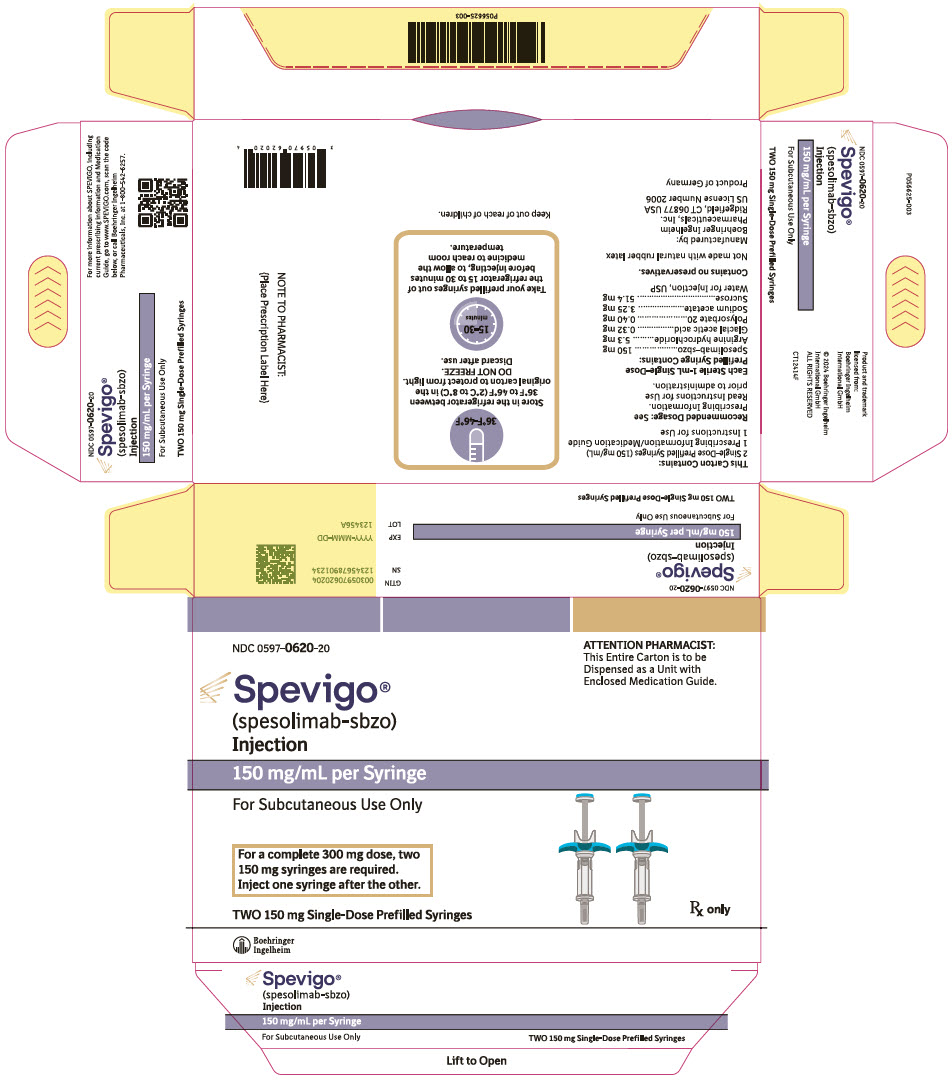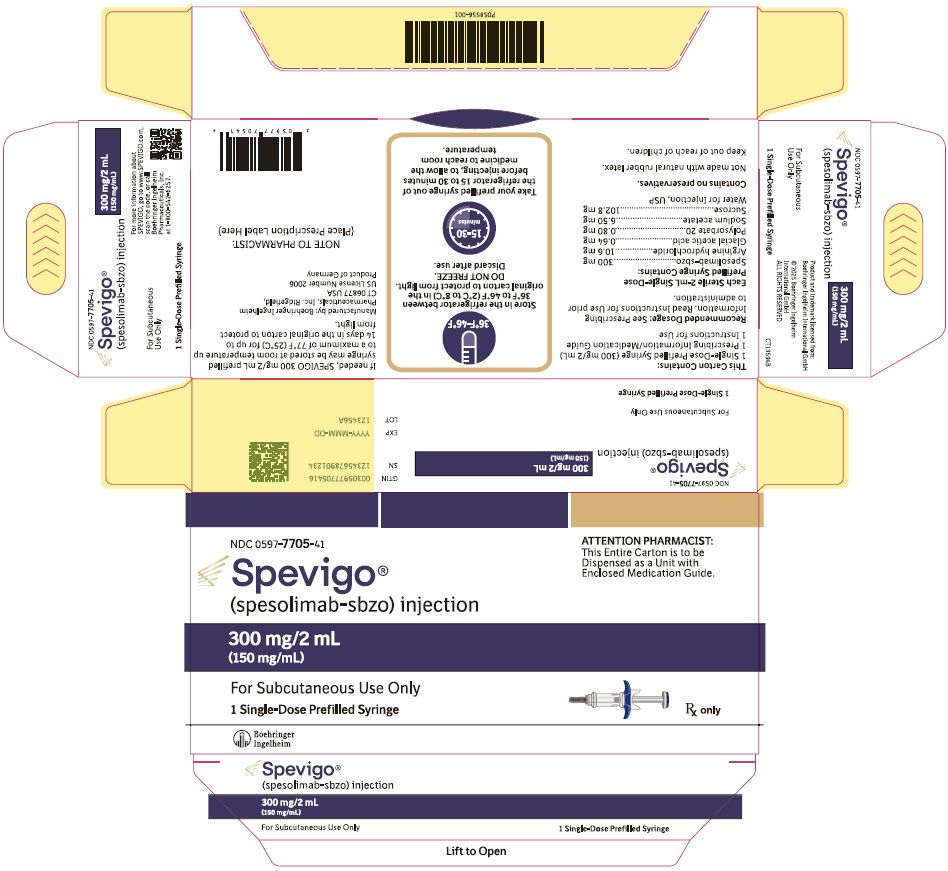 DRUG LABEL: SPEVIGO
NDC: 0597-0035 | Form: INJECTION
Manufacturer: Boehringer Ingelheim Pharmaceuticals, Inc.
Category: prescription | Type: HUMAN PRESCRIPTION DRUG LABEL
Date: 20251027

ACTIVE INGREDIENTS: SPESOLIMAB 60 mg/1 mL

HIGHLIGHTS OF PRESCRIBING INFORMATION

These highlights do not include all the information needed to use SPEVIGO safely and effectively. See full prescribing information for SPEVIGO.
SPEVIGO® (spesolimab-sbzo) injection, for subcutaneous or intravenous use
Initial U.S. Approval: 2022

RECENT MAJOR CHANGES

Dosage and Administration (2.2, 2.3, 2.5) | 05/2025
Contraindications (4) | 10/2025
Warnings and Precautions (5.3) | 10/2025

1 INDICATIONS AND USAGE

SPEVIGO is an interleukin-36 receptor antagonist indicated for the treatment of generalized pustular psoriasis (GPP) in adults and pediatric patients 12 years of age and older and weighing at least 40 kg. (1)

2 DOSAGE AND ADMINISTRATION

Subcutaneous Dosage for Treatment of GPP When Not Experiencing a Flare

Administer a subcutaneous loading dose of 600 mg, followed by 300 mg subcutaneously 4 weeks later and every 4 weeks thereafter. (2.3)

- Subcutaneous Use After Intravenous SPEVIGO for Treatment of GPP Flare: Four weeks after treatment with intravenous SPEVIGO, initiate or reinitiate subcutaneous SPEVIGO at a dose of 300 mg administered every 4 weeks. A loading dose is not required following treatment of a GPP flare with intravenous SPEVIGO. (2.3)
- See full prescribing information for preparation and administration instructions. (2.2, 2.5)

Intravenous Dosage for Treatment of GPP Flare

- Must be diluted before intravenous use. Administer as a single 900 mg dose by intravenous infusion over 90 minutes. If flare symptoms persist, may administer an additional intravenous 900 mg dose one week after the initial dose. (2.4)
- See full prescribing information for preparation and administration instructions and storage of the diluted solution. (2.2, 2.5)

3 DOSAGE FORMS AND STRENGTHS

For Subcutaneous Use

- Injection: 300 mg/2 mL (150 mg/mL) solution in a single-dose prefilled syringe (3)
- Injection: 150 mg/mL solution in a single-dose prefilled syringe (3)

For Intravenous Use

- Injection: 450 mg/7.5 mL (60 mg/mL) solution in a single-dose vial (3)

4 CONTRAINDICATIONS

Severe or life-threatening hypersensitivity to spesolimab-sbzo or to any of the excipients in SPEVIGO (4)

5 WARNINGS AND PRECAUTIONS

- Infections: SPEVIGO may increase the risk of infections. Treatment with SPEVIGO is not recommended during any clinically important active infection. Instruct patients to seek medical advice if signs or symptoms of clinically important infection occur during or after treatment. If a clinically important active infection develops, discontinue SPEVIGO until the infection resolves or is adequately treated. (5.1)
- Risk of Tuberculosis (TB): Evaluate patients for TB prior to initiating treatment with SPEVIGO. (5.2)
- Hypersensitivity and Infusion-Related Reactions: Hypersensitivity reactions, including anaphylaxis and drug reaction with eosinophilia and systemic symptoms (DRESS), and infusion-related reactions may occur. Discontinue SPEVIGO immediately and initiate appropriate treatment if a serious hypersensitivity reaction occurs. (5.3)
- Vaccinations: Avoid use of live vaccines during and for at least 16 weeks after treatment with SPEVIGO. (5.4)

6 ADVERSE REACTIONS

- Treatment of GPP When Not Experiencing a Flare: SPEVIGO has been associated with an increased incidence (≥9 cases per 100 patient-years) of injection site reaction, urinary tract infection, arthralgia, and pruritus. (6.1)
- Treatment of GPP Flare: The most common adverse reactions (≥5%) are asthenia and fatigue, headache, nausea, pruritus and prurigo, infusion site hematoma and bruising, and urinary tract infection. (6.1)

To report SUSPECTED ADVERSE REACTIONS, contact Boehringer Ingelheim Pharmaceuticals, Inc. at (800) 542-6257 or FDA at 1-800-FDA-1088 or www.fda.gov/medwatch.

FULL PRESCRIBING INFORMATION

1 INDICATIONS AND USAGE

SPEVIGO is indicated for the treatment of generalized pustular psoriasis (GPP) in adults and pediatric patients 12 years of age and older and weighing at least 40 kg.

2 DOSAGE AND ADMINISTRATION

2.1 Testing and Procedures Prior to Treatment Initiation

Evaluate patients for active or latent tuberculosis (TB) infection. SPEVIGO initiation is not recommended in patients with active TB infection. Consider initiating treatment of latent TB prior to initiation of SPEVIGO [see Warnings and Precautions (5.2)].

Complete all age-appropriate vaccinations according to current immunization guidelines prior to initiating SPEVIGO for treatment of GPP [see Warnings and Precautions (5.4)].

2.2 Important Administration Information

Subcutaneous Use for Treatment of GPP When Not Experiencing a Flare

- SPEVIGO prefilled syringes are for subcutaneous use for treatment of GPP when not experiencing a flare.
- When using SPEVIGO 300 mg/2 mL prefilled syringe:
  - If the healthcare professional determines that it is appropriate, a patient 12 years of age or older may self-inject or the caregiver may administer the loading dose and the subsequent doses of SPEVIGO after proper training in subcutaneous injection technique. In pediatric patients 12 years of age and older, administer SPEVIGO under the supervision of an adult.
- When using SPEVIGO 150 mg/mL prefilled syringe:
  - If required, the 600 mg subcutaneous loading dose of SPEVIGO is to be administered by a healthcare professional [see Dosage and Administration (2.3)].
  - For subsequent 300 mg doses, if the healthcare professional determines that it is appropriate, a patient 12 years of age or older may self-inject or the caregiver may administer SPEVIGO after proper training in subcutaneous injection technique. In pediatric patients 12 years of age and older, administer SPEVIGO under the supervision of an adult.
- If a patient experiences a GPP flare while receiving subcutaneous SPEVIGO, the GPP flare may be treated with intravenous SPEVIGO [see Dosage and Administration (2.4)].

Intravenous Use for Treatment of GPP Flare

- SPEVIGO vials are for intravenous use for treatment of GPP flare.
- Intravenous infusion of SPEVIGO is only to be administered by a healthcare professional in a healthcare setting. Prepare SPEVIGO intravenous infusion by diluting SPEVIGO single-dose vials [see Dosage and Administration (2.5)].
- Do not mix SPEVIGO with other medicinal products.

2.3 Recommended Subcutaneous Dosage for Treatment of GPP When Not Experiencing a Flare

The recommended dosage of SPEVIGO for treatment of GPP when not experiencing a flare in adults and pediatric patients 12 years of age and older and weighing at least 40 kg is a loading dose of 600 mg followed by 300 mg administered subcutaneously 4 weeks later and every 4 weeks thereafter.

Initiating or Reinitiating Subcutaneous SPEVIGO After Treatment of a GPP Flare with Intravenous SPEVIGO

Four weeks after treatment of a GPP flare with intravenous SPEVIGO [see Dosage and Administration (2.4)], initiate or reinitiate subcutaneous SPEVIGO for treatment of GPP at a dose of 300 mg administered every 4 weeks. A subcutaneous loading dose is not required following treatment of a GPP flare with intravenous SPEVIGO.

2.4 Recommended Intravenous Dosage for Treatment of GPP Flare

The recommended dosage of SPEVIGO for treatment of GPP flare in adults and pediatric patients 12 years of age and older and weighing at least 40 kg is a single 900 mg dose administered by intravenous infusion over 90 minutes.

If GPP flare symptoms persist, an additional intravenous 900 mg dose (over 90 minutes) may be administered one week after the initial dose.

2.5 Preparation and Administration Instructions

Parenteral drug products should be inspected visually for particulate matter and discoloration, whenever solution and container permits. SPEVIGO is a colorless to slightly brownish-yellow, clear to slightly opalescent solution. Do not use if the solution is cloudy, discolored, or contains large or colored particulates.

Prefilled Syringe (Subcutaneous Use for Treatment of GPP When Not Experiencing a Flare)

- Before subcutaneous injection, remove SPEVIGO prefilled syringes from the refrigerator and allow SPEVIGO to reach room temperature (15 to 30 minutes) without removing the needle cap.
- Administer SPEVIGO subcutaneously in the upper thighs or abdomen. Do not inject into areas where the skin is tender, bruised, erythematous, indurated, or scarred.
- If more than one injection is needed to achieve the recommended dose, administer each injection one right after the other. Choose a different injection site for each injection, at least 1 inch away from the other injection sites.
- Alternate between the upper thigh and abdomen injection sites for each complete dose.
- If a dose is missed, administer the dose as soon as possible. Thereafter, resume dosing at the regular scheduled time.
- The SPEVIGO "Instructions for Use" contains more detailed instructions on the preparation and administration of SPEVIGO [see Instructions for Use].

Vial (Intravenous Use for Treatment of GPP Flare)

Preparation

- SPEVIGO solution for intravenous infusion must be diluted before use.
- Use aseptic technique to prepare the solution for infusion.
- Draw and discard 15 mL from a 100 mL container of sterile 0.9% Sodium Chloride Injection.
- Slowly replace with 15 mL of SPEVIGO (two vials of 450 mg/7.5 mL).
- Mix gently before use.
- Use the diluted SPEVIGO solution immediately. If not administered immediately, refrigerate the diluted solution at 2°C to 8°C (36°F to 46°F) for no more than 4 hours. Protect from light.

Administration

- Administer SPEVIGO as a continuous intravenous infusion through an intravenous line containing a sterile, non-pyrogenic, low protein binding in-line filter (pore size of 0.2 micron) over 90 minutes.
- A pre-existing intravenous line may be used for administration of SPEVIGO. The line must be flushed with sterile 0.9% Sodium Chloride Injection prior to and at the end of infusion. No other infusion should be administered in parallel via the same intravenous access.
- If the infusion is slowed or temporarily stopped, the total infusion time (including stop time) should not exceed 180 minutes [see Warnings and Precautions (5.3)].
- No incompatibilities have been observed between SPEVIGO and infusion sets composed of polyvinylchloride (PVC), polyethylene (PE), polypropylene (PP), polybutadiene and polyurethane (PUR), and in-line filter membranes composed of polyethersulfone (PES, neutral and positively charged) and positively charged polyamide (PA).

3 DOSAGE FORMS AND STRENGTHS

SPEVIGO is a colorless to slightly brownish-yellow, clear to slightly opalescent solution available as:

For subcutaneous use:

- Injection: 300 mg/2 mL (150 mg/mL) solution in a single-dose prefilled syringe
- Injection: 150 mg/mL in a single-dose prefilled syringe

For intravenous use:

- Injection: 450 mg/7.5 mL (60 mg/mL) in a single-dose vial for dilution prior to intravenous infusion

4 CONTRAINDICATIONS

SPEVIGO is contraindicated in patients with severe or life-threatening hypersensitivity to spesolimab-sbzo or to any of the excipients in SPEVIGO. Reported hypersensitivity reactions have included drug reaction with eosinophilia and systemic symptoms (DRESS) and anaphylaxis [see Warnings and Precautions (5.3) and Adverse Reactions (6)].

5 WARNINGS AND PRECAUTIONS

5.1 Infections

SPEVIGO may increase the risk of infections. During the one-week placebo-controlled period in the Effisayil-1 trial, infections were reported in 14% of subjects treated with SPEVIGO compared with 6% of subjects treated with placebo [see Adverse Reactions (6.1)].

In patients with a chronic infection or a history of recurrent infection, consider the potential risks and expected clinical benefits of treatment prior to prescribing SPEVIGO. Treatment with SPEVIGO is not recommended in patients with any clinically important active infection until the infection resolves or is adequately treated. Instruct patients to seek medical advice if signs or symptoms of clinically important infection occur during or after treatment with SPEVIGO. If a patient develops a clinically important active infection, discontinue SPEVIGO therapy until the infection resolves or is adequately treated.

5.2 Risk of Tuberculosis

Evaluate patients for tuberculosis (TB) infection prior to initiating treatment with SPEVIGO. Avoid use of SPEVIGO in patients with active TB infection.

Consider initiating anti-TB therapy prior to initiating SPEVIGO in patients with latent TB or a history of TB in whom an adequate course of treatment cannot be confirmed. Monitor patients for signs and symptoms of active TB during and after SPEVIGO treatment.

5.3 Hypersensitivity and Infusion-Related Reactions

Serious hypersensitivity reactions, including anaphylaxis and delayed reactions such as drug reaction with eosinophilia and systemic symptoms (DRESS), have been reported during and following administration of SPEVIGO. These reactions can occur with the first dose or subsequent doses [see Adverse Reactions (6.1)].

SPEVIGO is contraindicated in patients with severe or life-threatening hypersensitivity to spesolimab-sbzo or to any of the excipients in SPEVIGO. If a patient develops signs of anaphylaxis or other serious hypersensitivity, discontinue SPEVIGO immediately and initiate appropriate treatment.

If a patient develops mild or moderate hypersensitivity during an intravenous infusion or other infusion-related reactions, stop SPEVIGO infusion and consider appropriate medical therapy (e.g., systemic antihistamines and/or corticosteroids). Upon resolution of the reaction, the infusion may be restarted at a slower infusion rate with gradual increase to complete the infusion.

5.4 Vaccinations

Prior to initiating SPEVIGO for treatment of GPP, complete all age-appropriate vaccinations according to current immunization guidelines.

Avoid use of live vaccines in patients during and for at least 16 weeks after treatment with SPEVIGO. No specific studies have been conducted in SPEVIGO-treated patients who have recently received live viral or live bacterial vaccines.

6 ADVERSE REACTIONS

The following adverse reactions are discussed in greater detail in other sections of the labeling:

- Infections [see Warnings and Precautions (5.1)]
- Hypersensitivity and Infusion-Related Reactions [see Warnings and Precautions (5.3)]

6.1 Clinical Trials Experience

Because clinical trials are conducted under widely varying conditions, adverse reaction rates observed in the clinical trials of a drug cannot be directly compared to rates in the clinical trials of another drug and may not reflect the rates observed in clinical practice.

Adverse Reactions with Intravenous SPEVIGO for Treatment of GPP Flare (Study Effisayil-1)

SPEVIGO was studied in Study Effisayil-1, a randomized, double-blind, placebo-controlled study comparing a single intravenous 900 mg dose of SPEVIGO (n=35) with placebo (n=18) in subjects with generalized pustular psoriasis (GPP) flare. Subjects in either treatment group who continued to experience flare symptoms at Week 1 were eligible to receive a single open-label intravenous dose of 900 mg of SPEVIGO (second dose and first dose for subjects in the SPEVIGO and placebo groups, respectively). At Week 1, 12 (34%) subjects and 15 subjects (83%) in the SPEVIGO and placebo groups, respectively, received open-label SPEVIGO. After Week 1 to Week 12, subjects in either treatment group whose GPP flare reoccurred after achieving a clinical response were eligible to receive a single open-label rescue intravenous dose of 900 mg of SPEVIGO, with a maximum of 3 total doses of SPEVIGO throughout the study. Six subjects received a single open-label rescue dose of SPEVIGO. Thirty-six subjects received 1 dose of SPEVIGO, 13 subjects received 2 doses of SPEVIGO, and 2 subjects received 3 doses of SPEVIGO throughout the study [see Clinical Studies (14)].

Subjects ranged in age from 21 to 69 years (mean age of 43 years); 45% were White and 55% were Asian; and 68% were female.

Table 1 summarizes selected adverse reactions that occurred at a rate of at least 1% and at a higher rate in the intravenous SPEVIGO group than in the placebo group through Week 1.

Table 1 Selected Adverse Reactions Occurring in ≥1% of the Intravenous SPEVIGO Group and More Frequently than in the Placebo Group through Week 1 in Subjects with GPP Flare (Study Effisayil-1)
Adverse Reaction | Intravenous SPEVIGO N = 35 n (%) | Placebo N = 18 n (%)
Asthenia and Fatigue | 3 (9) | 1 (6)
Headache | 3 (9) | 1 (6)
Nausea | 2 (6) | 0
Pruritus and prurigo | 2 (6) | 0
Infusion site hematoma and bruising | 2 (6) | 0
Urinary tract infection | 2 (6) | 0
Bacteremia | 1 (3) | 0
Bacteriuria | 1 (3) | 0
Cellulitis | 1 (3) | 0
Herpes dermatitis and oral herpes | 1 (3) | 0
Upper respiratory tract infection | 1 (3) | 0
Dyspnea | 1 (3) | 0
Eye edema | 1 (3) | 0
Urticaria | 1 (3) | 0

Specific Adverse Reactions

Infections

The most frequent adverse reactions that occurred in subjects treated with intravenous SPEVIGO were infections. During the 1-week placebo-controlled period in Study Effisayil-1, infections were reported in 14% of subjects treated with SPEVIGO compared with 6% of subjects treated with placebo. Serious infection (urinary tract infection) was reported in 1 subject (3%) treated with SPEVIGO and no subjects treated with placebo. Infections observed through Week 1 in Study Effisayil-1 in subjects treated with SPEVIGO were mild (29%) to moderate (71%).

Drug Reaction with Eosinophilia and Systemic Symptoms (DRESS)

Two cases of DRESS were reported in Study Effisayil-1 in subjects with GPP who were treated with intravenous SPEVIGO. RegiSCAR DRESS validation scoring (with the following categories: "no", "possible", "probable", or "definite" DRESS) was applied to the reported cases. Reported cases were assessed as "no DRESS" and "possible DRESS".

Safety through Week 12 and 17

In Study Effisayil-1, additional adverse reactions that occurred through Week 12 in subjects treated with 1 single intravenous dose of randomized SPEVIGO were mild to moderate infections: device-related infection (3%), subcutaneous abscess (3%), furuncle (3%), and influenza (3%).

Additional adverse reactions that occurred through Week 17 in subjects treated with a single intravenous dose of open-label SPEVIGO at Week 1 (second dose and first dose for subjects in the SPEVIGO and placebo groups, respectively) were mild to moderate infections: otitis externa (7%), vulvovaginal candidiasis (4%), vulvovaginal mycotic infection (4%), latent tuberculosis (4%), diarrhea (11%), and gastritis (4%). No new adverse reactions were identified for up to 16 weeks in subjects treated with a single intravenous dose of open-label rescue SPEVIGO from Week 1 to Week 12 (range 1-3 total doses).

Adverse Reactions with Subcutaneous SPEVIGO for Treatment of GPP When Not Experiencing a Flare (Study Effisayil-2)

Subcutaneous treatment with SPEVIGO was studied in Study Effisayil-2, a randomized, placebo-controlled, double-blind, parallel group study evaluating three dosages of SPEVIGO or placebo in subjects with generalized pustular psoriasis (GPP). Subjects were randomized (1:1:1:1) to receive a 600 mg loading dose (LD) of SPEVIGO followed by 300 mg every 4 weeks (n=30), one of two other dosages of SPEVIGO, or placebo (n=30) for up to 48 weeks [see Clinical Studies (14)].

Subjects ranged in age from 14 to 75 years (mean age was 40 years); 64% of subjects were Asian and 36% were White; 62% of subjects were female.

Regarding the exposure-adjusted incidence rates for subjects on randomized treatment prior to receiving rescue treatment for flare or completing trial without a flare, the rate per 100-patient years for injection site reaction (including erythema, pain, swelling, induration, urticaria, and warmth at the injection site) was 31.6 for the subcutaneous SPEVIGO cohort (600 mg LD followed by 300 mg every 4 weeks) compared to 12.7 for the placebo cohort.

Regarding the exposure-adjusted incidence rates for subjects on randomized treatment prior to receiving rescue treatment for flare or completing trial without a flare, the rate per 100-patient years for urinary tract infection was 18 for the subcutaneous SPEVIGO cohort (600 mg LD followed by 300 mg every 4 weeks) compared to 0 for the placebo cohort.

Regarding the exposure-adjusted incidence rates for subjects on randomized treatment prior to receiving rescue treatment for flare or completing trial without a flare, the rate per 100-patient years for pruritus was 8.8 for the subcutaneous SPEVIGO cohort (600 mg LD followed by 300 mg every 4 weeks) compared to 0 for the placebo cohort.

Regarding the exposure-adjusted incidence rates for subjects on randomized treatment prior to receiving rescue treatment for flare or completing trial without a flare, the rate per 100-patient years for arthralgia was 13.3 for the subcutaneous SPEVIGO cohort (600 mg LD followed by 300 mg every 4 weeks) compared to 6 for the placebo cohort.

For subjects on randomized treatment prior to receiving rescue treatment for flare or completing trial without flare, there were 3 subjects who discontinued subcutaneous SPEVIGO in the subcutaneous SPEVIGO cohort (600 mg LD followed by 300 mg every 4 weeks) due to treatment emergent adverse events of psoriasis compared to no subjects in the placebo cohort who discontinued placebo for any treatment emergent adverse event.

Safety In Study Effisayil-2 after flare

In Effisayil-2, subjects who experienced a GPP flare and received at least one dose of an open-label single intravenous 900 mg dose of SPEVIGO were treated with open-label subcutaneous SPEVIGO 300 mg. These subjects (n=19) received subcutaneous dosing at every 12 weeks which could have been increased to every 4 weeks based on GPPPGA total score or pustulation sub score increased by ≥1 from any previous OL maintenance visit. The reported safety profile of open-label subcutaneous SPEVIGO use after treatment of GPP flare with open-label intravenous SPEVIGO use was consistent with the safety profiles of use of SPEVIGO from Trial Effisayil-1 and randomized controlled data from Trial Effisayil-2.

Clinical Development of Spesolimab-sbzo

Guillain-Barre syndrome

Among approximately 835 subjects exposed to spesolimab-sbzo during clinical development, Guillain-Barre syndrome (GBS) was reported in 3 subjects who received various doses of spesolimab-sbzo via various methods of administration in clinical studies for unapproved indications.

6.2 Postmarketing Experience

The following adverse reactions have been identified during postapproval use of SPEVIGO. Because these reactions are reported voluntarily from a population of uncertain size, it is not always possible to reliably estimate their frequency or establish a causal relationship to drug exposure.

Immune System Disorders: Immediate systemic hypersensitivity reactions, including anaphylaxis.

8 USE IN SPECIFIC POPULATIONS

8.1 Pregnancy

Risk Summary

The limited data on the use of SPEVIGO in pregnant women are insufficient to inform a drug-associated risk of adverse pregnancy-related outcomes. Human IgG is known to cross the placental barrier; therefore, SPEVIGO may be transmitted from the mother to the developing fetus. In an animal reproduction study, intravenous administration of a surrogate antibody against IL36R in mice during the period of organogenesis did not elicit any reproductive toxicity (see Data).

The background risk of major birth defects and miscarriage for the indicated population is unknown. All pregnancies have a background risk of birth defect, loss, or other adverse outcomes. In the U.S. general population, the estimated background risk of major birth defects and miscarriage in clinically recognized pregnancies is 2% to 4% and 15% to 20%, respectively.

Data

Animal Data

Embryo-fetal development and pre- and postnatal development toxicity studies were performed in mice using a surrogate mouse specific IL36R antagonist monoclonal antibody. In the embryo-fetal development study, the surrogate was administered intravenously at doses up to 50 mg/kg to pregnant female mice twice weekly during the period of organogenesis. The surrogate was not associated with embryo-fetal lethality or fetal malformations. In the pre- and postnatal development toxicity study, the surrogate was administered intravenously at doses up to 50 mg/kg to pregnant female mice twice weekly from gestation day 6 through lactation day 18. There were no maternal effects observed. There were no treatment-related effects observed on postnatal developmental, neurobehavioral, or reproductive performance of offspring.

8.2 Lactation

Risk Summary

There are no data on the presence of spesolimab-sbzo in human milk, the effects on the breastfed infant, or the effects on milk production. Spesolimab-sbzo is a monoclonal antibody and is expected to be present in human milk. The developmental and health benefits of breastfeeding should be considered along with the mother's clinical need for SPEVIGO and any potential adverse effects on the breastfed infant from SPEVIGO or from the underlying maternal condition.

8.4 Pediatric Use

The safety and effectiveness of SPEVIGO for the treatment of GPP have been established in pediatric patients 12 years of age and older and weighing at least 40 kg. Use of SPEVIGO for this indication is supported by data from a randomized, placebo-controlled study which included 6 pediatric subjects 14 to 17 years of age with a history of GPP treated with subcutaneous SPEVIGO (Study Effisayil-2) and evidence from an adequate and well-controlled study of intravenous SPEVIGO in adults with GPP (Study Effisayil-1), with additional pharmacokinetic analyses showing similar drug exposure levels in adults and pediatric subjects 12 years of age and older and weighing 40 kg or more [see Adverse Reactions (6.1), Clinical Pharmacology (12.3), and Clinical Studies (14)].

The safety and effectiveness of SPEVIGO in pediatric patients younger than 12 years of age or in pediatric patients weighing less than 40 kg have not been established.

8.5 Geriatric Use

There were 2 (6%) intravenous SPEVIGO-treated subjects 65 to 74 years of age and no subjects 75 years of age or older in Study Effisayil-1. There were 6 (7%) subcutaneous SPEVIGO-treated subjects 65 to 74 years of age and 1 (1%) subject 75 years of age in Study Effisayil-2. Clinical studies of SPEVIGO did not include sufficient numbers of subjects 65 years of age and older to determine whether they respond differently from younger adult subjects.

11 DESCRIPTION

Spesolimab-sbzo, an interleukin-36 receptor antagonist, is a humanized monoclonal IgG1 antibody (mAb) against human IL-36R produced in Chinese hamster ovary (CHO) cells by recombinant DNA technology. Spesolimab-sbzo has a molecular weight of approximately 146 kDa.

SPEVIGO (spesolimab-sbzo) injection is a sterile, preservative-free, colorless to slightly brownish-yellow, clear to slightly opalescent solution supplied in a single-dose prefilled syringe for subcutaneous use. Each 2 mL prefilled syringe contains 300 mg spesolimab-sbzo, arginine hydrochloride (10.6 mg), glacial acetic acid (0.64 mg), polysorbate 20 (0.80 mg), sodium acetate (6.50 mg), sucrose (102.8 mg), and Water for Injection, USP with a pH of 5.2 to 5.8. Each 1 mL prefilled syringe contains 150 mg spesolimab-sbzo, arginine hydrochloride (5.3 mg), glacial acetic acid (0.32 mg), polysorbate 20 (0.40 mg), sodium acetate (3.25 mg), sucrose (51.4 mg), and Water for Injection, USP with a pH of 5.2 to 5.8.

SPEVIGO (spesolimab-sbzo) injection is a sterile, preservative-free, colorless to slightly brownish-yellow, clear to slightly opalescent solution supplied in a single-dose vial for intravenous use. Each 7.5 mL vial contains 450 mg spesolimab-sbzo, arginine hydrochloride (39.5 mg), glacial acetic acid (2.4 mg), polysorbate 20 (3.0 mg), sodium acetate (24.5 mg), sucrose (386 mg), and Water for Injection, USP with a pH of 5.2 to 5.8.

12 CLINICAL PHARMACOLOGY

12.1 Mechanism of Action

Spesolimab-sbzo is a humanized monoclonal immunoglobulin G1 antibody that inhibits interleukin-36 (IL-36) signaling by specifically binding to the IL36R. Binding of spesolimab-sbzo to IL36R prevents the subsequent activation of IL36R by its ligands (IL-36 α, β and γ) and downstream activation of pro-inflammatory and pro-fibrotic pathways. The precise mechanism linking reduced IL36R activity and the treatment of flares of GPP is unclear.

12.2 Pharmacodynamics

The pharmacodynamics of SPEVIGO in the treatment of patients with GPP have not been fully characterized.

12.3 Pharmacokinetics

A population pharmacokinetic model was developed based on data collected from healthy subjects, patients with GPP, and patients with other diseases. After a single intravenous dose of 900 mg of SPEVIGO, the population PK model-estimated AUC0-∞ (95% CI) and Cmax (95% CI) in a typical anti-drug antibody (ADA)-negative patient with GPP were 4750 (4510, 4970) mcg∙day/mL and 238 (218, 256) mcg/mL, respectively. After subcutaneous SPEVIGO 600 mg LD followed by 300 mg every 4 weeks, the mean steady-state trough concentration ranged from 33.4 mcg/mL to 42.3 mcg/mL.

When administered intravenously, spesolimab-sbzo AUC increased dose-proportionally from 0.3 to 20 mg/kg, and CL and terminal half-life were independent of dose. Following subcutaneous single dose administration, spesolimab-sbzo exposure increased slightly more than dose-proportionally across the dose range of 150 mg to 600 mg due to increased bioavailability at higher doses.

Absorption

Following subcutaneous single dose administration of SPEVIGO in healthy volunteers, peak plasma concentrations were achieved between 5.5 to 7 days after dosing. After subcutaneous administration in the abdomen, absolute bioavailability (90% CI) was slightly higher at higher doses with estimated values of 58 (51, 66)%, 65 (60, 69)%, and 72 (65, 79)% at 150 mg, 300 mg, and 600 mg, respectively. Based on limited data, absolute bioavailability (90% CI) in the thigh was approximately 85 (77, 94)% following a subcutaneous dose of 300 mg SPEVIGO.

Distribution

Based on the population pharmacokinetic analysis, the typical total volume of distribution at steady state was 6.4 L.

Elimination

Metabolism

The metabolic pathway of spesolimab-sbzo has not been characterized. As a humanized IgG1 monoclonal antibody, spesolimab-sbzo is expected to be degraded into small peptides and amino acids via catabolic pathways in a manner similar to endogenous IgG.

Excretion

In the linear dose range (0.3 to 20 mg/kg), based on the population PK model, spesolimab-sbzo clearance (95% CI) in a typical GPP patient without ADA, weighing 70 kg was 0.184 (0.175, 0.194) L/day. The terminal half-life was 25.5 (24.4, 26.3) days.

Specific Populations

Age, Gender, and Race

Based on population pharmacokinetic analyses, age, gender, and race did not have an effect on the pharmacokinetics of spesolimab-sbzo.

Hepatic and Renal Impairment

As a monoclonal antibody, spesolimab-sbzo is not expected to undergo hepatic or renal elimination. No formal study of the effect of hepatic or renal impairment on the pharmacokinetics of spesolimab-sbzo was conducted.

Body Weight

Spesolimab-sbzo concentrations were increased in subjects with lower body weight and decreased in subjects with higher body weight. The clinical impact of body weight on spesolimab-sbzo plasma concentrations is unknown.

Pediatric Patients

The pharmacokinetics of spesolimab-sbzo have not been studied in pediatric subjects below the age of 12 years. The plasma pharmacokinetics of spesolimab-sbzo observed in pediatric subjects 12 years of age and older and weighing 40 kg or more following subcutaneous administration were consistent with that observed in adults.

Drug Interaction Studies

No formal drug interactions studies have been conducted with spesolimab-sbzo. In patients with GPP, spesolimab-sbzo is not expected to cause cytokine-mediated CYP interactions as a perpetrator.

12.6 Immunogenicity

The observed incidence of anti-drug antibodies is highly dependent on the sensitivity and specificity of the assay. Differences in assay methods preclude meaningful comparisons of the incidence of anti-drug antibodies in the studies described below with the incidence of anti-drug antibodies in other studies, including those of spesolimab-sbzo or of other spesolimab products.

In subjects with GPP treated with intravenous SPEVIGO in Study Effisayil-1, ADAs formed with a median onset of 2.3 weeks. Following administration of 900 mg intravenous SPEVIGO, (12/50) 24% of subjects had a maximum ADA titer greater than 4000 and were neutralizing antibody (Nab)-positive by the end of the study (Weeks 12 to 17). In Study Effisayil-2, ADAs formed with a median onset of 8 weeks. Following administration of a 600 mg subcutaneous LD of SPEVIGO followed by 300 mg every 4 weeks for a total duration of 48 weeks, 24% of subjects had a maximum ADA titer greater than 4000 and were Nab-positive.

In Study Effisayil-1 following intravenous SPEVIGO, females appeared to have higher immunogenicity response; the percentage of subjects with ADA titer greater than 4000 was 30% in females, and 12% in males, respectively. In Study Effisayil-2 following administration of subcutaneous SPEVIGO, the data on immunogenicity response in males versus females were inconclusive.

Anti-Drug Antibody Effects on Pharmacokinetics

In subjects with ADA titers below 4000, there was no apparent impact on spesolimab-sbzo pharmacokinetics. In some subjects with ADA titer values greater than 4000, plasma spesolimab-sbzo concentrations were significantly reduced after reaching this ADA titer.

In Study Effisayil-1, there are limited data on the impact of ADAs on safety and efficacy upon retreatment as the majority of subjects did not experience a subsequent, new flare in an open-label extension study.

In subjects who received SPEVIGO 600 mg subcutaneous LD followed by 300 mg every 4 weeks in Study Effisayil-2, the mean trough concentrations beginning at Week 8 in ADA-positive subjects with titers greater than 4000 were approximately 77% to 107% of trough concentrations in subjects who were ADA-negative or ADA-positive with titer values less than 4000. After subcutaneous administration of SPEVIGO, there appears to be no impact of ADA presence on efficacy. This observation is based on limited numbers of ADA-positive subjects (N=11). There are insufficient data to assess whether there is a clinically significant effect of ADAs on the safety of spesolimab-sbzo.

13 NONCLINICAL TOXICOLOGY

13.1 Carcinogenesis, Mutagenesis, Impairment of Fertility

Carcinogenicity and mutagenicity studies have not been conducted with spesolimab-sbzo.

No adverse effects on fertility were observed in male or female mice that were intravenously administered a surrogate antibody to IL36R at doses up to 50 mg/kg twice weekly.

14 CLINICAL STUDIES

Intravenous SPEVIGO for Treatment of GPP Flare (Study Effisayil-1)

A randomized, double-blind, placebo-controlled study (Study Effisayil-1) [NCT03782792] was conducted to evaluate the clinical efficacy and safety of intravenous SPEVIGO in adult subjects with flares of generalized pustular psoriasis (GPP). Subjects were randomized if they had a flare of GPP of moderate-to-severe intensity, as defined by:

- A Generalized Pustular Psoriasis Physician Global Assessment (GPPPGA) total score of at least 3 (moderate) [the total GPPPGA score ranges from 0 (clear) to 4 (severe)],
- The presence of fresh pustules (new appearance or worsening of pustules),
- GPPPGA pustulation sub score of at least 2 (mild), and
- At least 5% of body surface area covered with erythema and the presence of pustules.

Subjects were required to discontinue systemic and topical therapy for GPP prior to receiving study drug.

A total of 53 subjects were randomized (2:1) to receive a single intravenous dose of 900 mg SPEVIGO (N=35) or placebo (N=18) (administered over 90 minutes) during the double-blind portion of the study.

The study population consisted of 32% male and 68% female. The mean age was 43 years (range: 21 to 69 years); 55% of subjects were Asian and 45% were White. For ethnicity, there were no subjects that identified as Hispanic or Latino in the study. Most subjects included in the study had a GPPPGA pustulation sub score of 3 (43%) or 4 (36%), and subjects had a GPPPGA total score of 3 (81%) or 4 (19%). In this study, 25% of subjects had been previously treated with biologic therapy for GPP. At baseline acute flare, of the subjects with white blood cell count (WBC) assessments, 45% and 31% of subjects in the intravenous SPEVIGO and placebo groups, respectively, had (WBC) >12 × 10^9/L. Seventeen percent and 11% of subjects in the intravenous SPEVIGO and placebo groups, respectively, had temperature >38° Celsius. Of the subjects with WBC assessments, 12% and 6% of subjects in the SPEVIGO and placebo groups, respectively, had both WBC >12 × 10^9/L and temperature >38° Celsius [see Adverse Reactions (6.1)].

The primary endpoint of the study was the proportion of subjects with a GPPPGA pustulation sub score of 0 (indicating no visible pustules) at Week 1 after treatment.

Clinical Response

The results of the primary endpoint are presented in Table 2.

Table 2 GPPPGA Pustulation Sub Score at Week 1 in Adult Subjects with Flares of GPP in Study Effisayil-1 (Intravenous SPEVIGO)
 | Intravenous SPEVIGO (N=35) | Placebo (N=18)
Subjects achieving a GPPPGA pustulation sub score of 0, n (%) | 19 (54) | 1 (6)
Risk difference versus placebo, % (95% CI) | 49 (21, 67)
GPPPGA = Generalized Pustular Psoriasis Physician Global Assessment

In Study Effisayil-1, subjects in either treatment group who continued to experience flare symptoms at Week 1 were eligible to receive a single open-label intravenous dose of 900 mg of SPEVIGO (second dose and first dose for subjects in the SPEVIGO and placebo groups, respectively). At Week 1, 12 (34%) subjects and 15 subjects (83%) in the intravenous SPEVIGO and placebo groups, respectively, received open-label SPEVIGO. In subjects who were randomized to intravenous SPEVIGO and received an open-label dose of SPEVIGO at Week 1, 5 (42%) subjects had a GPPPGA pustulation sub score of 0 at Week 2 (one week after their second dose of SPEVIGO).

This study did not include sufficient numbers of subjects to determine if there are differences in response according to biological sex, age, race, baseline GPPPGA pustulation sub score, and baseline GPPPGA total score.

Subcutaneous SPEVIGO for Treatment of GPP When Not Experiencing a Flare (Study Effisayil-2)

A randomized, double-blind, placebo-controlled study (Study Effisayil-2) [NCT04399837] evaluated the efficacy and safety of SPEVIGO for subcutaneous administration in adults and pediatric subjects (12 years of age and older and weighing at least 40 kg) with a history of at least two GPP flares of moderate-to-severe intensity in the past. Subjects were randomized if they had a GPPPGA total score of 0 or 1 at screening and randomization. Subjects were required to discontinue systemic and topical therapy for GPP prior to or at randomization. These subjects must have had a history of flaring while on concomitant treatment for GPP or a history of flaring upon dose reduction or discontinuation of these concomitant medications.

A total of 123 subjects were randomized (1:1:1:1) to one of four treatment arms:

- SPEVIGO: 600 mg subcutaneous loading dose (LD) followed by 300 mg subcutaneously every 4 weeks
- SPEVIGO: 600 mg subcutaneous LD followed by 300 mg subcutaneously every 12 weeks
- SPEVIGO: 300 mg subcutaneous LD followed by 150 mg subcutaneously every 12 weeks
- Placebo: subcutaneous LD followed by subcutaneous treatment every 4 weeks

While a 600 mg LD dose of SPEVIGO followed by 300 mg every 12 weeks dosage and a 300 mg LD of SPEVIGO followed by 150 mg every 12 weeks dosage were studied in Study Effisayil-2, these dosages are not approved. The recommended dosage of SPEVIGO for treatment of GPP when not experiencing a flare is a subcutaneous LD of 600 mg followed by 300 mg subcutaneously, administered every 4 weeks [see Dosage and Administration (2.3)]. The results summarized in Table 3 are those for the recommended dosage regimen.

The study population was 38% male and 62% female. The mean age was 40 years old (range: 14 to 75 years) with 8 (7%) pediatric subjects (2 per treatment arm); 64% of subjects were Asian and 36% were White. For ethnicity, 6% of subjects identified as Hispanic or Latino. Subjects included in the study had a GPPPGA pustulation sub score of 1 (28%) or 0 (72%), and subjects had a GPPPGA total score of 1 (86%) or 0 (14%). At the time of randomization, 75% of subjects were treated with systemic therapy for GPP, which was discontinued at the start of the randomized study treatment.

Subjects who experienced a GPP flare were eligible to receive up to two open-label intravenous doses of 900 mg SPEVIGO [see Dosage and Administration (2.4)]. Two (7%) subjects in the subcutaneous SPEVIGO 600 mg LD/300 mg every 4 weeks arm and 15 (48%) subjects in the placebo arm received intravenous SPEVIGO for treatment of GPP flare.

The primary endpoint of the study was the time to the first GPP flare up to Week 48 (defined by a GPPPGA pustulation sub score of ≥2 and an increase in GPPPGA total score by ≥2 from baseline). The key secondary endpoint was the occurrence of at least one GPP flare up to Week 48.

Clinical Response

The number of subjects who experienced at least one GPP flare and the time to first GPP flare are presented in Table 3 and Figure 1.

Table 3 Occurrence of at Least One GPP Flare up to Week 48 in Adults and Pediatric Subjects (12 Years of Age and Older and Weighing At Least 40 kg) With a History of GPP in Study Effisayil-2 (Subcutaneous SPEVIGO)
 | Subcutaneous SPEVIGO 600 mg LD, followed by 300 mg every 4 weeks (N=30) | Placebo (N=31)
Subjects with GPP flares, n (%)* | 3 (10) | 16 (52)
Risk difference for GPP flare occurrence vs placebo,% (95% CI) | -39 (-62, -16)
*The use of intravenous SPEVIGO treatment or investigator-prescribed standard of care to treat GPP worsening were considered as onset of GPP flare

Figure 1 Time to First GPP Flare up to Week 48 in Adults and Pediatric Subjects (12 Years of Age and Older and Weighing At Least 40 kg) With a History of GPP in Study Effisayil-2 (Subcutaneous SPEVIGO)

The results of the primary and key secondary endpoints were generally consistent across subgroups including biological sex, age, race, BMI, body weight, mutation status in IL36RN, concurrent plaque psoriasis, GPPPGA total score at baseline, and irrespective of any systemic GPP treatment at randomization.

16 HOW SUPPLIED/STORAGE AND HANDLING

How Supplied

SPEVIGO (spesolimab-sbzo) injection is a sterile, preservative-free, colorless to slightly brownish-yellow, clear to slightly opalescent solution available as follows:

Prefilled syringes (for subcutaneous use)

- NDC Number 0597-7705-41: Each carton contains one single-dose 300 mg/2 mL (150 mg/mL) prefilled syringe.
- NDC Number 0597-7705-72: Each carton contains two single-dose 300 mg/2 mL (150 mg/mL) prefilled syringes.
- NDC Number 0597-0620-20: Each carton contains two single-dose 150 mg/mL prefilled syringes.

Single-dose vials (for intravenous use)

- NDC Number 0597-0035-10: Each carton contains two single-dose 450 mg/7.5 mL (60 mg/mL) glass vials.

Storage and Handling

Prefilled syringes

300 mg/2 mL:

- Store SPEVIGO prefilled syringes refrigerated between 2°C to 8°C (36°F to 46°F) in original carton to protect from light. Do not freeze. Do not use if frozen even if it has been thawed.
- If needed, SPEVIGO 300 mg/2 mL prefilled syringes may be stored at room temperature up to a maximum of 25°C (77°F) for up to 14 days in the original carton to protect from light. Discard SPEVIGO 300 mg/2 mL prefilled syringes if kept at room temperature for more than 14 days.

150 mg/mL:

- Store SPEVIGO prefilled syringes refrigerated between 2°C to 8°C (36°F to 46°F) in original carton to protect from light. Do not freeze. Do not use if frozen even if it has been thawed.

Single-dose vials

- Store SPEVIGO vials refrigerated between 2°C to 8°C (36°F to 46°F) in original carton to protect from light. Do not freeze.
- Prior to use, may store unopened SPEVIGO vials at room temperature, 20°C to 25°C (68°F to 77°F), for up to 24 hours in the original carton to protect from light.

17 PATIENT COUNSELING INFORMATION

Advise the patient to read the FDA-approved patient labeling (Medication Guide and Instructions for Use).

Infections

Inform patients that SPEVIGO may lower the ability of their immune system to fight infections. Instruct patients of the importance of communicating any history of infections to the healthcare provider and contacting their healthcare provider if they develop any signs or symptoms of clinically important infection during or after treatment with SPEVIGO [see Warnings and Precautions (5.1)].

Hypersensitivity and Infusion-Related Reactions

Inform patients that hypersensitivity and infusion-related reactions may occur with SPEVIGO. Advise patients to seek immediate medical attention if they experience any symptoms of a serious hypersensitivity reaction [see Warnings and Precautions (5.3)].

Vaccinations

Advise patients to avoid receiving live vaccines during and for at least 16 weeks after treatment with SPEVIGO. Instruct patients to inform the healthcare provider that they are taking SPEVIGO prior to a potential vaccination [see Warnings and Precautions (5.4)].

Administration Instructions for Subcutaneous SPEVIGO for Treatment of GPP When Not Experiencing a Flare

If a patient 12 years of age and older or caregiver is to administer subcutaneous SPEVIGO, instruct them on injection technique and assess their ability to inject subcutaneously to ensure the proper administration of SPEVIGO. Provide training to patients or caregivers on preparation and administration of subcutaneous SPEVIGO and on proper needle and syringe disposal [see Dosage and Administration (2.5) and Instructions for Use].

If more than one injection is needed to achieve the recommended dose, instruct patients to administer each injection subcutaneously one right after the other and to choose a different injection site for each injection, at least 1 inch away from the other injection sites [see Dosage and Administration (2.5) and Instructions for Use].

Manufactured by:
Boehringer Ingelheim Pharmaceuticals, Inc.
Ridgefield, CT 06877 USA
US License Number 2006

Licensed from:
Boehringer Ingelheim International GmbH, Ingelheim, Germany

SPEVIGO is a registered trademark of and used under license from Boehringer Ingelheim International GmbH.
Copyright © 2025 Boehringer Ingelheim International GmbH
ALL RIGHTS RESERVED
COL9614EJ222025
SPL9616H

MEDICATION GUIDE
SPEVIGO® (spea VEE go)
(spesolimab-sbzo)
injection, for subcutaneous or intravenous use

What is the most important information I should know about SPEVIGO?
SPEVIGO may cause serious side effects, including:

- Infections. SPEVIGO may lower the ability of your or your child's immune system to fight infections and may increase your or your child's risk of infections. Your healthcare provider should check you or your child for infections and tuberculosis (TB) before starting treatment with SPEVIGO and may treat you or your child for TB before you begin treatment with SPEVIGO if you have a history of TB or have active TB. Your healthcare provider should watch you or your child closely for signs and symptoms of TB during or after treatment with SPEVIGO. Tell your healthcare provider right away if you or your child have an infection or have symptoms of an infection during or after treatment with SPEVIGO, including:

- fevers, chills, or sweats
- muscle aches
- cough
- shortness of breath

- blood in your phlegm (mucus)
- burning when you urinate
- urinating more often than normal

- Allergic reactions and infusion-related reactions. Serious allergic reactions may happen during or after your or your child's SPEVIGO injection. If you or your child have a serious allergic reaction, your healthcare provider will stop treatment with SPEVIGO. If you or your child are given SPEVIGO in a vein (intravenously) and have an infusion-related reaction, your healthcare provider will stop your or your child's SPEVIGO infusion and treat your or your child's symptoms and may restart SPEVIGO at a slower infusion rate.
  Tell your healthcare provider or get emergency medical help right away if you or your child get any of the following symptoms during or after your or your child's SPEVIGO injection:

- feeling faint, dizzy, or lightheaded
- swelling of your face, eyelids, lips, mouth, tongue, or throat
- trouble breathing or throat tightness
- fever
- mouth sores

- chest tightness
- hives or skin rash that is different than the rash from generalized pustular psoriasis (GPP)
- itching
- swollen lymph nodes

See "What are the possible side effects of SPEVIGO?" for more information about side effects.

What is SPEVIGO?
SPEVIGO is a prescription medicine used to treat generalized pustular psoriasis (GPP) in adults and children 12 years of age and older who weigh at least 88 pounds (40 kg).
It is not known if SPEVIGO is safe and effective in children under 12 years of age or who weigh less than 88 pounds (40 kg).

Do not receive SPEVIGO if you or your child have had a severe or life-threatening allergic reaction to spesolimab-sbzo or any of the ingredients in SPEVIGO. See the end of this Medication Guide for a complete list of ingredients in SPEVIGO.

Before you or your child receive SPEVIGO, tell your healthcare provider about all of your medical conditions, including if you or your child:

- have an infection that does not go away or that keeps coming back. See "What is the most important information I should know about SPEVIGO?"
- have TB or have been in close contact with someone with TB.
- have recently received or are scheduled to receive an immunization (vaccine). You or your child should not receive live vaccines during and for at least 16 weeks after treatment with SPEVIGO. You or your child should be brought up to date with all vaccines before starting SPEVIGO.
- are pregnant or plan to become pregnant. It is not known if SPEVIGO can harm your or your child's unborn baby.
- are breastfeeding or plan to breastfeed. It is not known if SPEVIGO passes into your breast milk. Talk to your healthcare provider about the best way to feed your or your child's baby during treatment with SPEVIGO.

Tell your healthcare provider about all the medicines you or your child take, including prescription and over-the-counter medicines, vitamins, and herbal supplements.

How will I receive SPEVIGO?
When given under the skin (subcutaneously) for treatment of GPP when not experiencing a flare:

- Read the detailed "Instructions for Use" that comes with SPEVIGO for information on how to prepare and inject a dose of SPEVIGO and how to properly throw away (dispose of) used SPEVIGO prefilled syringes.
- SPEVIGO prefilled syringes come in two different strengths (300 mg/2 mL or 150 mg/mL). Your healthcare provider will prescribe the prefilled syringe that is right for you.
- Your healthcare provider will tell you how much SPEVIGO to inject and when to inject it. Use SPEVIGO exactly as your healthcare provider tells you to use it.
- If your healthcare provider decides that you or a caregiver can give your or your child's injections of SPEVIGO at home, you should receive training on the right way to prepare and inject SPEVIGO. Do not try to inject SPEVIGO until you have been shown the right way by your healthcare provider. In children 12 years of age and older, SPEVIGO should be given under the supervision of an adult.
- If you miss a dose of SPEVIGO, inject your or your child's dose as soon as possible. Then, inject your or your child's next dose at the regular scheduled time. In case you are not sure when to inject SPEVIGO, call your healthcare provider.

When given in a vein (intravenously) for GPP flare treatment:

- Your healthcare provider will give you or your child SPEVIGO through a needle placed in your vein (intravenous infusion) over 90 minutes.
- SPEVIGO is usually given one time. If GPP flare symptoms continue, your healthcare provider will decide if you should receive an additional treatment with SPEVIGO after 1 week.

What are the possible side effects of SPEVIGO?
SPEVIGO may cause serious side effects.

- See "What is the most important information I should know about SPEVIGO?"

The most common side effects of SPEVIGO for GPP flare treatment include:

- feeling tired or weak
- headache
- nausea

- itching or itchy bumps
- a collection of blood under the skin at the infusion site or bruising
- urinary tract infection

The most common side effects of SPEVIGO for treatment of GPP when not experiencing a flare include:

- redness, pain, swelling, hardening, hives, or warmth at the injection site
- urinary tract infection

- joint pain
- itching

These are not all of the possible side effects of SPEVIGO.
Call your doctor for medical advice about side effects. You may report side effects to FDA at 1-800-FDA-1088.

How should I store SPEVIGO?

- Store SPEVIGO prefilled syringes in the refrigerator between 36°F to 46°F (2°C to 8°C).
- Do not freeze SPEVIGO. Do not use SPEVIGO if frozen, even if it has been thawed.
- Store SPEVIGO in the original carton until use to protect from light.
- If needed, SPEVIGO 300 mg/2 mL prefilled syringes may also be stored at room temperature up to 77°F (25°C) for up to 14 days. Throw away (dispose of) SPEVIGO 300 mg/2 mL prefilled syringes that have been left at room temperature for more than 14 days.

Keep SPEVIGO and all medicines out of the reach of children.

General information about the safe and effective use of SPEVIGO.
Medicines are sometimes prescribed for purposes other than those listed in a Medication Guide. Do not use SPEVIGO for a condition for which it was not prescribed. Do not give SPEVIGO to other people, even if they have the same symptoms that you have. It may harm them. You can ask your pharmacist or healthcare provider for information about SPEVIGO that is written for health professionals.

What are the ingredients in SPEVIGO?
Active ingredient: spesolimab-sbzo
Inactive ingredients: arginine hydrochloride, glacial acetic acid, polysorbate 20, sodium acetate, sucrose, and Water for Injection

Manufactured by: Boehringer Ingelheim Pharmaceuticals, Inc., Ridgefield, CT 06877 USA
US License Number 2006
Licensed from: Boehringer Ingelheim International GmbH, Ingelheim, Germany
SPEVIGO is a registered trademark of and used under license from Boehringer Ingelheim International GmbH.
Copyright © 2025 Boehringer Ingelheim International GmbH ALL RIGHTS RESERVED
COL9614CD222025
For more information about SPEVIGO, including current prescribing information and Medication Guide, go to www.SPEVIGO.com, scan the code below, or call Boehringer Ingelheim Pharmaceuticals, Inc. at 1-800-542-6257.

This Medication Guide has been approved by the U.S. Food and Drug Administration.

Revised: 05/2025

INSTRUCTIONS FOR USE SPEVIGO® (spea VEE go) (spesolimab-sbzo) injection, for subcutaneous use 150 mg/mL Two 150 mg/mL single-dose prefilled syringes for a total of 300 mg dose

This Instructions for Use contains information on how to inject SPEVIGO.

Read both sides of this Instructions for Use before you use SPEVIGO for the first time and each time you get a refill. There may be new information. This information does not take the place of talking to your healthcare provider about your or your child's medical condition or treatment. Your healthcare provider should show you or your child the right way to inject SPEVIGO before you try to inject yourself or your child for the first time. In children 12 years of age and older, SPEVIGO should be given under the supervision of an adult.

SPEVIGO is for one-time use only. Do not reuse the prefilled syringes.

Your healthcare provider has prescribed a dose of SPEVIGO for you or your child that requires 2 injections (2 prefilled syringes) to deliver a complete dose.

You must inject the contents of both SPEVIGO prefilled syringes that come in the carton to deliver the complete dose.

Getting to know SPEVIGO:

SPEVIGO comes in a prefilled syringe with a safety cover. The needle is pulled back into the safety cover after injection.

Guide to parts:

The figure below shows SPEVIGO before use, and after use with the activated safety cover.

Important information you need to know before injecting SPEVIGO:

- You must inject the contents of both SPEVIGO prefilled syringes to deliver a complete dose.
- Inspect the SPEVIGO carton to be sure that you have the correct medicine, 2 prefilled syringes for your or your child's prescribed dose, for any damage, and the expiration date (EXP).
- Do not use SPEVIGO if the liquid is cloudy or contains flakes or large or colored particles.
- Do not use SPEVIGO if the expiration date (EXP) has passed.
- Do not use SPEVIGO if the prefilled syringe has been dropped.
- Do not remove the cap until you are ready to inject.
- Inject SPEVIGO under the skin (subcutaneous injection) in either the upper thighs or stomach-area (abdomen). Do not inject SPEVIGO into any other area of the body.

Storing SPEVIGO:

- Store SPEVIGO prefilled syringes in the refrigerator between 36°F to 46°F (2°C to 8°C).
- Do not freeze SPEVIGO. Do not use SPEVIGO if frozen, even if it has been thawed.
- Store SPEVIGO in the original carton until use to protect from light.

Keep SPEVIGO and all medicines out of the reach of children.

Step 1

Gather supplies

- Take the SPEVIGO carton out of the refrigerator and remove the prefilled syringes from the carton.
- Gather supplies listed above and place them on a clean, flat work surface in a well-lit area.
- If you do not have all the supplies listed above, contact your pharmacist.

- See Step 10: "Throwing away (disposing of) the used SPEVIGO prefilled syringes and caps."

Step 2

Preparing to inject SPEVIGO

- Wait 15 to 30 minutes to allow the medicine to reach room temperature to avoid discomfort during injection. Do not speed up the warming process in any way, such as using the microwave or placing the syringe in warm water.
- Do not leave the prefilled syringes in direct sunlight.
- Do not remove the needle cap until you are ready to inject.
- Wash your hands well with soap and water and dry them.

Step 3

Inspecting the prefilled syringes

Check both prefilled syringes now:

- Check to make sure the medicine name SPEVIGO and the dose on your prefilled syringes match your or your child's prescribed dose.
- Check the expiration date (EXP) on both prefilled syringes. Do not use if the expiration date has passed.
- Check both prefilled syringes for damage, cracks, and leakage. Do not use if any part of the prefilled syringes appear cracked, broken, or are leaking.
- Make sure the medicine in both prefilled syringes is clear and colorless to slightly brownish-yellow. It may contain tiny white or clear particles. Do not use if the medicine is cloudy or has flakes or large or colored particles in it.
- It is normal to see air bubbles, they do not need to be removed.
- Do not use if the SPEVIGO prefilled syringes have been dropped.

Preparing for your first injection

Prepare for the first of 2 injections.
You will repeat the following steps with the second syringe right away after your first injection.
2 injections are needed for a complete dose.

Step 4

Choosing the injection site

Choose an injection site.

- You may use an area on your:
  - upper thighs or
  - stomach-area (abdomen), except for an area 2 inches around your navel (belly button).
- Choose a different injection site each time you inject, at least 1 inch away from the last injection site. Alternate between upper thigh or stomach-area for each complete dose.
- Do not inject an area near your waistline or belly button.
- Do not inject into areas that are tender, bruised, red, hard, or scarred.
- Do not inject through clothes.

Step 5

Clean the injection site

- Clean the injection site with an alcohol wipe and let air dry.
- Do not touch this area again before injecting.
- Do not fan or blow on the clean area.

Step 6

Removing the cap from the prefilled syringe

- Hold the prefilled syringe by the finger grip with one hand. With the other hand, pull the cap straight off.
  - Do not pull on or hold the plunger rod.
  - Do not twist the cap. Twisting the cap could damage the needle.
  - Do not use the prefilled syringe if the needle is bent or damaged. If you accidentally bend the needle, do not attempt to straighten it.
- Throw away the cap. See Step 10: "Throwing away (disposing of) the used SPEVIGO prefilled syringes and caps."
- Proceed to the next step right away after removing the cap.
  - Do not try to recap the needle. Re-capping can lead to needle stick injury.
  - Do not touch the needle or let the needle touch anything before injecting.

Step 7

Pinch the skin

- Gently pinch the area of cleaned skin around your injection site and hold it firmly.
- Keep the skin pinched during the entire injection. You will inject into the pinched skin.
- Do not let go until your injection is complete. See Step 8C: "Checking injection is complete."

Step 8

Injecting SPEVIGO

A. Inserting the needle:

- Hold the prefilled syringe by the blue finger grip. Avoid touching the blue thumb pad.
- Using a quick, "dart-like" motion, insert the needle into the pinched skin at about a 45-degree angle.
- Do not move the needle while inserting or during the injection.

B. Injecting the medicine:

- Use your thumb to slowly press down on the blue thumb pad to push the plunger rod down inside the syringe body.
- Continue pressing on the blue thumb pad until the plunger rod has moved all the way down.
- Make sure that the blue thumb pad cannot be pressed any further so that the built-in safety cover can be activated.

C. Checking injection is complete:

- Slowly remove your thumb from the blue thumb pad, to move the needle out of your skin and up into the safety cover.
  - Check that the thumb pad springs back and that the needle is inside the safety cover.
  - If the needle is not inside the safety cover, call your healthcare provider. You may not have received a full dose.
- If there is bleeding, press a cotton ball or gauze on the site for a few seconds.
- Do not rub the injection site.
- Apply an adhesive bandage if needed.

Important: Do not move the prefilled syringe when inserting the needle into your skin, while injecting, or when removing the needle from your skin.

Step 9

Second injection

- Choose a different injection site.
  The new injection site should be at least 1 inch away from last injection site. Alternate between upper thigh or stomach-area for each complete dose.
- Get second prefilled syringe.
- Repeat steps 4 through 8 right away.
- Then continue to step 10.

Important:
You must inject the contents of both SPEVIGO prefilled syringes to give a complete dose.

Step 10

Throwing away (disposing of) the used SPEVIGO prefilled syringes and caps

- Put the used prefilled syringes and caps in an FDA-cleared sharps disposal container right away after use.
- If you do not have an FDA-cleared sharps disposal container, you may use a household container that is:
  - made of a heavy-duty plastic,
  - can be closed with a tight fitting, puncture-resistant lid, without sharps being able to come out,
  - upright and stable during use,
  - leak resistant, and
  - properly labeled to warn of hazardous waste inside the container.

When your sharps disposal container is almost full, you will need to follow your community guidelines for the right way to dispose of your sharps disposal container. There may be state or local laws about how you should throw away used needles and syringes. For more information about safe sharps disposal, and for specific information about sharps disposal in the state that you live in, go to the FDA's website at: http://www.fda.gov/safesharpsdisposal.

- Do not reuse the prefilled syringes.
- Do not throw away (dispose of) your used sharps disposal container in your household trash unless your community guidelines permit this.
- Do not recycle your used sharps disposal container.

Important: Always keep the sharps disposal container out of the reach of children.

If you have any problems with your injection, do not use another SPEVIGO prefilled syringe. Call your healthcare provider or pharmacist for help.
For more information call 1-800-542-6257.

Manufactured by:
Boehringer Ingelheim Pharmaceuticals, Inc., Ridgefield, CT 06877 USA
US License Number 2006

Licensed from: Boehringer Ingelheim International GmbH, Ingelheim, Germany
SPEVIGO is a registered trademark of and used under license from Boehringer Ingelheim International GmbH.

Copyright © 2025 Boehringer Ingelheim International GmbH ALL RIGHTS RESERVED
COL12534BE292025

For more information about SPEVIGO, including current prescribing information and Medication Guide, go to www.SPEVIGO.com, scan the code below, or call Boehringer Ingelheim Pharmaceuticals, Inc. at 1-800-542-6257.

This Instructions for Use has been approved by the U.S. Food and Drug Administration.
Revised: 05/2025

INSTRUCTIONS FOR USE SPEVIGO® (spea VEE go) (spesolimab-sbzo) injection, for subcutaneous use 300 mg/2 mL One 300 mg/2 mL single-dose prefilled syringe for a total of 300 mg dose

This Instructions for Use contains information on how to inject SPEVIGO.

Read both sides of this Instructions for Use before you use SPEVIGO for the first time and each time you get a refill. There may be new information. This information does not take the place of talking to your healthcare provider about your or your child's medical condition or treatment. Your healthcare provider should show you or your child the right way to inject SPEVIGO before you try to inject yourself or your child for the first time. In children 12 years of age and older, SPEVIGO should be given under the supervision of an adult.

SPEVIGO is for one-time use only. Do not reuse the prefilled syringe.

Your healthcare provider has prescribed a dose of SPEVIGO for you or your child that requires 1 injection to deliver a complete dose.

You must inject the contents of the SPEVIGO prefilled syringe that comes in the carton to deliver the complete dose.

Getting to know SPEVIGO:

SPEVIGO comes in a prefilled syringe with a safety cover. The needle is pulled back into the safety cover after injection.

Guide to parts:

The figure below shows SPEVIGO before use, and after use with the activated safety cover.

Important information you need to know before injecting SPEVIGO

- Inspect the SPEVIGO carton to be sure that you have the correct medicine, 1 prefilled syringe for your or your child's prescribed dose, for any damage, and the expiration date (EXP).
- Do not use SPEVIGO if the liquid is cloudy or contains flakes or large or colored particles.
- Do not use SPEVIGO if the expiration date (EXP) has passed.
- Do not use SPEVIGO if the prefilled syringe has been dropped.
- Do not remove the cap until you are ready to inject.
- Inject SPEVIGO under the skin (subcutaneous injection) in either the upper thighs or stomach-area (abdomen). Do not inject SPEVIGO into any other area of the body.

Storing SPEVIGO:

- Store SPEVIGO prefilled syringes in the refrigerator between 36°F to 46°F (2°C to 8°C).
- Do not freeze SPEVIGO. Do not use SPEVIGO if frozen, even if it has been thawed.
- Store SPEVIGO in the original carton until use to protect from light.
- If needed, SPEVIGO 300 mg/2 mL prefilled syringe may also be stored at room temperature up to 77°F (25°C) for up to 14 days.
- Throw away (dispose of) SPEVIGO 300 mg/2 mL prefilled syringe that has been left at room temperature for more than 14 days.

Keep SPEVIGO and all medicines out of the reach of children.

Step 1

Gather supplies

- Take the SPEVIGO carton out of the refrigerator and remove the prefilled syringe from the carton.
- Gather supplies listed above and place them on a clean, flat work surface in a well-lit area.
- If you do not have all the supplies listed above, contact your pharmacist.

- See Step 9: "Throwing away (disposing of) the used SPEVIGO prefilled syringe and cap."

Step 2

Preparing to inject SPEVIGO

- Wait 15 to 30 minutes to allow the medicine to reach room temperature to avoid discomfort during injection.
- Do not speed up the warming process in any way, such as using the microwave or placing the syringe in warm water.
- Do not leave the prefilled syringe in direct sunlight.
- Do not remove the needle cap until you are ready to inject.
- Wash your hands well with soap and water and dry them.

Step 3

Inspecting the prefilled syringe

Check the prefilled syringe:

- Check to make sure the medicine name SPEVIGO and the dose on the prefilled syringe match your or your child's prescribed dose.
- Check the expiration date (EXP) on the prefilled syringe. Do not use if the expiration date has passed.
- Check the prefilled syringe for damage, cracks, and leakage. Do not use if any part of the prefilled syringe appears cracked, broken, or is leaking.
- Make sure the medicine in the prefilled syringe is clear and colorless to slightly brownish-yellow. It may contain tiny white or clear particles. Do not use if the medicine is cloudy or has flakes or large or colored particles in it.
- It is normal to see air bubbles, they do not need to be removed.

Step 4

Choosing the injection site

Choose an injection site.

- You may use an area on your:
  - upper thighs or
  - stomach-area (abdomen), except for an area 2 inches around your navel (belly button).
- Choose a different injection site each time you inject at least 1 inch away from the last injection site. Alternate between upper thigh or stomach-area for each complete dose.
- Do not inject into an area near your waistline or belly button.
- Do not inject into areas that are tender, bruised, red, hard, or scarred.
- Do not inject through clothes.

Step 5

Clean the injection site

- Clean the injection site with an alcohol wipe and let air dry.
- Do not touch this area again before injecting.
- Do not fan or blow on the clean area.

Step 6

Removing the cap from the prefilled syringe

- Hold the prefilled syringe by the finger grip with one hand. With the other hand, pull the cap straight off.
  - Do not pull on or hold the plunger rod.
  - Do not twist the cap. Twisting the cap could damage the needle.
  - Do not use the prefilled syringe if the needle is bent or damaged. If you accidentally bend the needle, do not attempt to straighten it.
- Throw away the cap. See Step 9: "Throwing away (disposing of) the used SPEVIGO prefilled syringes and caps."
- Proceed to the next step right away after removing the cap.
  - Do not try to recap the needle. Re-capping can lead to needle stick injury.
  - Do not touch the needle or let the needle touch anything before injecting.

Step 7

Pinch the skin

- Gently pinch the area of cleaned skin around your injection site and hold it firmly.
- Keep the skin pinched during the entire injection.
- Do not let go until your injection is complete. See Step 8C: "Checking injection is complete."

Step 8

Injecting SPEVIGO

A. Inserting the needle:

- Hold the prefilled syringe by the finger grip.
- Do not touch the thumb pad yet.
- Using a quick, "dart-like" motion, insert the needle into the pinched skin at about a 45-degree angle.
- Do not move the needle while inserting or during the injection.

B. Injecting the medicine:

- Use your thumb to slowly press down on the thumb pad to push the plunger rod down inside the syringe body.
- Continue pressing on the thumb pad until the plunger rod has moved all the way down.
- Make sure that the thumb pad cannot be pressed any further so that you can activate the built-in safety cover.

C. Checking injection is complete:

- Slowly remove your thumb from the thumb pad to move the needle out of your skin and up into the safety cover.
  - Check that the thumb pad springs back and that the needle is inside the safety cover.
  - If the needle is not inside the safety cover, call your healthcare provider. You may not have received a full dose.
- If there is bleeding, press a cotton ball or gauze on the site for a few seconds.
- Do not rub the injection site.
- Apply an adhesive bandage if needed.

Important: Do not move the prefilled syringe when inserting the needle into your skin, while injecting, or when removing the needle from your skin.

Step 9

Throwing away (disposing of) the used SPEVIGO prefilled syringe and cap

- Put the used prefilled syringe and cap in an FDA-cleared sharps disposal container right away after use.
- If you do not have an FDA-cleared sharps disposal container, you may use a household container that is:
  - made of a heavy-duty plastic,
  - can be closed with a tight fitting, puncture-resistant lid, without sharps being able to come out,
  - upright and stable during use,
  - leak resistant, and
  - properly labeled to warn of hazardous waste inside the container.

When your sharps disposal container is almost full, you will need to follow your community guidelines for the right way to dispose of your sharps disposal container. There may be state or local laws about how you should throw away used needles and syringes. For more information about safe sharps disposal, and for specific information about sharps disposal in the state that you live in, go to the FDA's website at: http://www.fda.gov/safesharpsdisposal.

- Do not reuse the prefilled syringe.
- Do not throw away (dispose of) your used sharps disposal container in your household trash unless your community guidelines permit this.
- Do not recycle your used sharps disposal container.

Important: Always keep the sharps disposal container out of the reach of children.

If you have any problems with your injection, do not use another SPEVIGO prefilled syringe. Call your healthcare provider or pharmacist for help.
For more information call 1-800-542-6257.

Manufactured by:
Boehringer Ingelheim Pharmaceuticals, Inc., Ridgefield, CT 06877 USA
US License Number 2006

Licensed from: Boehringer Ingelheim International GmbH, Ingelheim, Germany
SPEVIGO is a registered trademark of and used under license from Boehringer Ingelheim International GmbH.

Copyright © 2025 Boehringer Ingelheim International GmbH ALL RIGHTS RESERVED
COL13636AE292025

For more information about SPEVIGO, including current prescribing information and Medication Guide, go to www.SPEVIGO.com, scan the code below, or call Boehringer Ingelheim Pharmaceuticals, Inc. at 1-800-542-6257.

This Instructions for Use has been approved by the U.S. Food and Drug Administration.
Issued: 05/2025

INSTRUCTIONS FOR USE SPEVIGO® (spea VEE go) (spesolimab-sbzo) injection, for subcutaneous use 300 mg/2 mL Two 300 mg/2 mL single-dose prefilled syringes for a total of 600 mg dose

This Instructions for Use contains information on how to inject SPEVIGO.

Read both sides of this Instructions for Use before you use SPEVIGO for the first time and each time you get a refill. There may be new information. This information does not take the place of talking to your healthcare provider about your or your child's medical condition or treatment. Your healthcare provider should show you or your child the right way to inject SPEVIGO before you try to inject yourself or your child for the first time. In children 12 years of age and older, SPEVIGO should be given under the supervision of an adult.

SPEVIGO is for one-time use only. Do not reuse the prefilled syringes.

Your healthcare provider has prescribed a dose of SPEVIGO for you or your child that requires 2 injections (2 prefilled syringes) to deliver a complete dose.

You must inject the contents of both SPEVIGO prefilled syringes that come in the carton to deliver the complete dose.

Getting to know SPEVIGO:

SPEVIGO comes in a prefilled syringe with a safety cover. The needle is pulled back into the safety cover after injection.

Guide to parts:

The figure below shows SPEVIGO before use, and after use with the activated safety cover.

Important information you need to know before injecting SPEVIGO

- You must inject the contents of both SPEVIGO prefilled syringes to deliver a complete dose.
- Inspect the SPEVIGO carton to be sure that you have the correct medicine, 2 prefilled syringes for your or your child's prescribed dose, for any damage, and the expiration date (EXP).
- Do not use SPEVIGO if the liquid is cloudy or contains flakes or large or colored particles.
- Do not use SPEVIGO if the expiration date (EXP) has passed.
- Do not use SPEVIGO if the prefilled syringe has been dropped.
- Do not remove the cap until you are ready to inject.
- Inject SPEVIGO under the skin (subcutaneous injection) in either the upper thighs or stomach-area (abdomen). Do not inject SPEVIGO into any other area of the body.

Storing SPEVIGO

- Store SPEVIGO prefilled syringes in the refrigerator between 36°F to 46°F (2°C to 8°C).
- Do not freeze SPEVIGO. Do not use SPEVIGO if frozen, even if it has been thawed.
- Store SPEVIGO in the original carton until use to protect from light.
- If needed, SPEVIGO 300 mg/2 mL prefilled syringe may also be stored at room temperature up to 77°F (25°C) for up to 14 days.
- Throw away (dispose of) SPEVIGO 300 mg/2 mL prefilled syringe that has been left at room temperature for more than 14 days.

Keep SPEVIGO and all medicines out of the reach of children.

Step 1

Gather supplies

- Take the SPEVIGO carton out of the refrigerator and remove the prefilled syringes from the carton.
- Gather supplies listed above and place them on a clean, flat work surface in a well-lit area.
- If you do not have all the supplies listed above, contact your pharmacist.

- See Step 10: "Throwing away (disposing of) the used SPEVIGO prefilled syringes and caps."

Step 2

Preparing to inject SPEVIGO

- Wait 15 to 30 minutes to allow the medicine to reach room temperature to avoid discomfort during injection.
- Do not speed up the warming process in any way, such as using the microwave or placing the syringe in warm water.
- Do not leave the prefilled syringe in direct sunlight.
- Do not remove the needle cap until you are ready to inject.
- Wash your hands well with soap and water and dry them.

Step 3

Inspecting the prefilled syringes

Check both prefilled syringes now:

- Check to make sure the medicine name SPEVIGO and the dose on your prefilled syringes match your or your child's prescribed dose.
- Check the expiration date (EXP) on both prefilled syringes. Do not use if the expiration date has passed.
- Check both prefilled syringes for damage, cracks, and leakage. Do not use if any part of the prefilled syringes appear cracked, broken, or are leaking.
- Make sure the medicine in both prefilled syringes is clear and colorless to slightly brownish-yellow. It may contain tiny white or clear particles. Do not use if the medicine is cloudy or has flakes or large or colored particles in it.
- It is normal to see air bubbles, they do not need to be removed.

Preparing for your first injection

Prepare for the first of 2 injections.
You will repeat the following steps with the second syringe right away after your first injection.
2 injections are needed for a complete dose.

Step 4

Choosing the injection site

Choose an injection site.

- You may use an area on your:
  - upper thighs or
  - stomach-area (abdomen), except for an area 2 inches around your navel (belly button).
- Choose a different injection site each time you inject, at least 1 inch away from the last injection site. Alternate between upper thigh or stomach-area for each complete dose.
- Do not inject into an area near your waistline or belly button.
- Do not inject into areas that are tender, bruised, red, hard, or scarred.
- Do not inject through clothes.

Step 5

Clean the injection site

- Clean the injection site with an alcohol wipe and let air dry.
- Do not touch this area again before injecting.
- Do not fan or blow on the clean area.

Step 6

Removing the cap from the prefilled syringe

- Hold the prefilled syringe by the finger grip with one hand. With the other hand, pull the cap straight off.
  - Do not pull on or hold the plunger rod.
  - Do not twist the cap. Twisting the cap could damage the needle.
  - Do not use the prefilled syringe if the needle is bent or damaged. If you accidentally bend the needle, do not attempt to straighten it.
- Throw away the cap. See Step 10: "Throwing away (disposing of) the used SPEVIGO prefilled syringes and caps."
- Proceed to the next step right away after removing the cap.
  - Do not try to recap the needle. Re-capping can lead to needle stick injury.
  - Do not touch the needle or let the needle touch anything before injecting.

Step 7

Pinch the skin

- Gently pinch the area of cleaned skin around your injection site and hold it firmly.
- Keep the skin pinched during the entire injection.
- Do not let go until your injection is complete. See Step 8C: "Checking injection is complete."

Step 8

Injecting SPEVIGO

A. Inserting the needle:

- Hold the prefilled syringe by the finger grip.
- Do not touch the thumb pad yet.
- Using a quick, "dart-like" motion, insert the needle into the pinched skin at about a 45-degree angle.
- Do not move the needle while inserting or during the injection.

B. Injecting the medicine:

- Use your thumb to slowly press down on the thumb pad to push the plunger rod down inside the syringe body.
- Continue pressing on the thumb pad until the plunger rod has moved all the way down.
- Make sure that the thumb pad cannot be pressed any further so that you can activate the built-in safety cover.

C. Checking injection is complete:

- Slowly remove your thumb from the thumb pad, to move the needle out of your skin and up into the safety cover.
  - Check that the thumb pad springs back and that the needle is inside the safety cover.
  - If the needle is not inside the safety cover, call your healthcare provider. You may not have received a full dose.
- If there is bleeding, press a cotton ball or gauze on the site for a few seconds.
- Do not rub the injection site.
- Apply an adhesive bandage if needed.

Important: Do not move the prefilled syringe when inserting the needle into your skin, while injecting, or when removing the needle from your skin.

Step 9

Second injection

- Choose a different injection site.
  The new injection site should be at least 1 inch away from last injection site. Alternate between upper thigh or stomach-area for each complete dose.
- Get second prefilled syringe.
- Repeat steps 4 through 8 right away.
- Then continue to step 10.

Important:
You must inject the contents of both SPEVIGO prefilled syringes to give a complete dose.

Step 10

Throwing away (disposing of) the used SPEVIGO prefilled syringes and caps

- Put the used prefilled syringes and caps in an FDA-cleared sharps disposal container right away after use.
- If you do not have an FDA-cleared sharps disposal container, you may use a household container that is:
  - made of a heavy-duty plastic,
  - can be closed with a tight fitting, puncture-resistant lid, without sharps being able to come out,
  - upright and stable during use,
  - leak resistant, and
  - properly labeled to warn of hazardous waste inside the container.

When your sharps disposal container is almost full, you will need to follow your community guidelines for the right way to dispose of your sharps disposal container. There may be state or local laws about how you should throw away used needles and syringes. For more information about safe sharps disposal, and for specific information about sharps disposal in the state that you live in, go to the FDA's website at: http://www.fda.gov/safesharpsdisposal.

- Do not reuse the prefilled syringes.
- Do not throw away (dispose of) your used sharps disposal container in your household trash unless your community guidelines permit this.
- Do not recycle your used sharps disposal container.

Important: Always keep the sharps disposal container out of the reach of children.

If you have any problems with your injection, do not use another SPEVIGO prefilled syringe. Call your healthcare provider or pharmacist for help.
For more information call 1-800-542-6257.

Manufactured by:
Boehringer Ingelheim Pharmaceuticals, Inc., Ridgefield, CT 06877 USA
US License Number 2006

Licensed from: Boehringer Ingelheim International GmbH, Ingelheim, Germany
SPEVIGO is a registered trademark of and used under license from Boehringer Ingelheim International GmbH.

Copyright © 2025 Boehringer Ingelheim International GmbH ALL RIGHTS RESERVED
COL13635AE292025

For more information about SPEVIGO, including current prescribing information and Medication Guide, go to www.SPEVIGO.com, scan the code below, or call Boehringer Ingelheim Pharmaceuticals, Inc. at 1-800-542-6257.

This Instructions for Use has been approved by the U.S. Food and Drug Administration.
Issued: 05/2025

PRINCIPAL DISPLAY PANEL - 450 mg/7.5 mL Vial Carton

NDC 0597-0035-10
Rx only

DISPENSE WITH ENCLOSED MEDICATION GUIDE

Spevigo®
(spesolimab-sbzo)
Injection

450 mg/7.5 mL per vial
(60 mg/mL)

For Intravenous Infusion after Dilution
Discard Unused Portion

Prepare both vials in carton for
a complete dose of 900 mg

Contents: contains TWO - 450 mg/7.5 mL single-dose vials

Boehringer
Ingelheim

PRINCIPAL DISPLAY PANEL - 150 mg Syringe Carton

NDC 0597-0620-20

ATTENTION PHARMACIST:
This Entire Carton is to be
Dispensed as a Unit with
Enclosed Medication Guide.

Spevigo®
(spesolimab-sbzo)
Injection

150 mg/mL per Syringe

For Subcutaneous Use Only

For a complete 300 mg dose, two
150 mg syringes are required.
Inject one syringe after the other.

TWO 150 mg Single-Dose Prefilled Syringes

Rx only

Boehringer
Ingelheim

PRINCIPAL DISPLAY PANEL - 300 mg/2 mL Syringe Carton

NDC 0597-7705-41

ATTENTION PHARMACIST:
This Entire Carton is to be
Dispensed as a Unit with
Enclosed Medication Guide.

Spevigo®
(spesolimab-sbzo) injection

300 mg/2 mL
(150 mg/mL)

For Subcutaneous Use Only

1 Single-Dose Prefilled Syringe

Rx only

Boehringer
Ingelheim